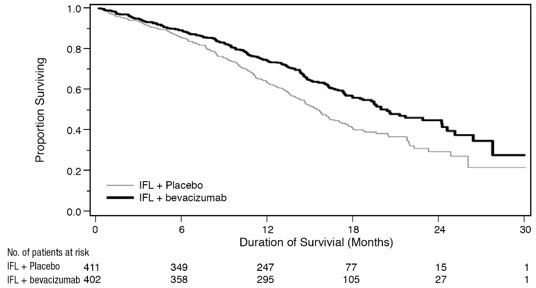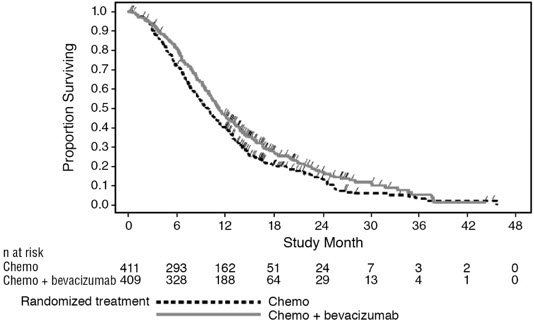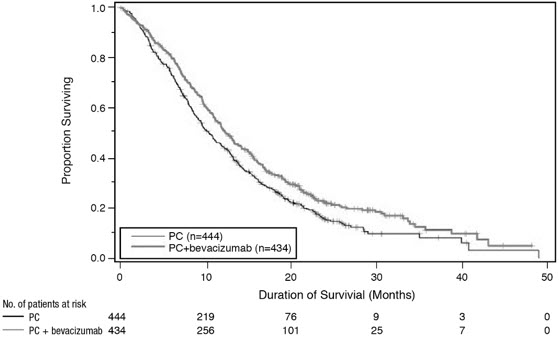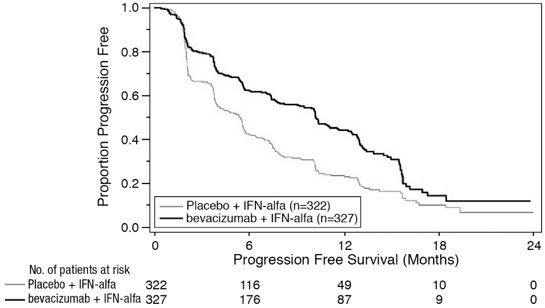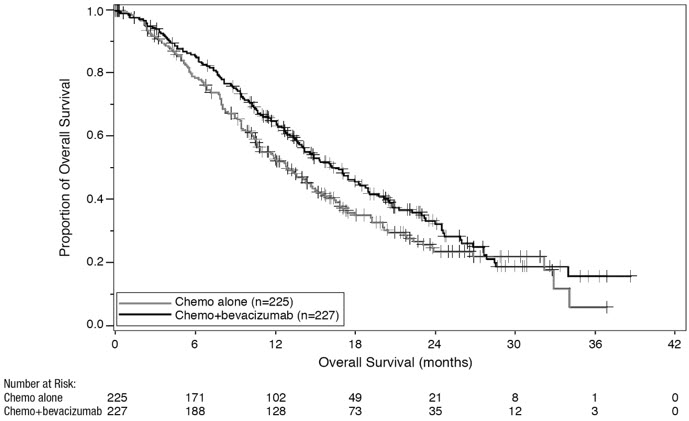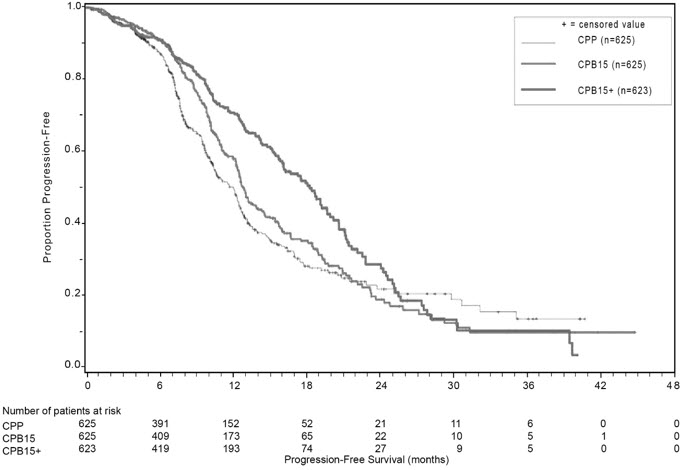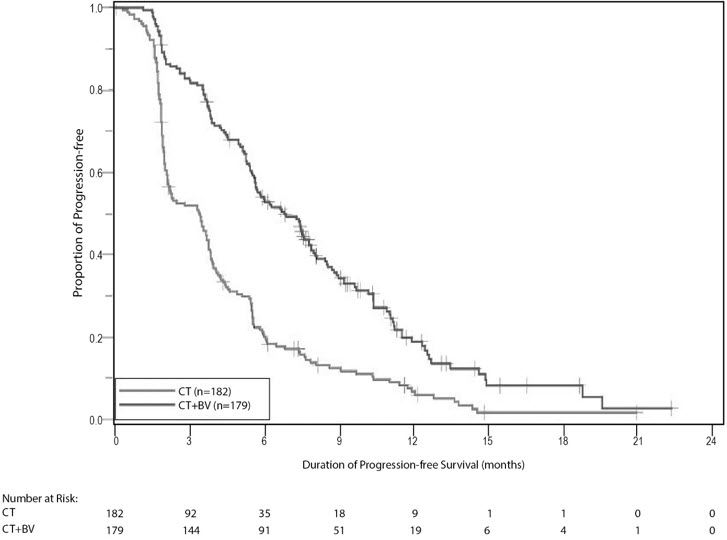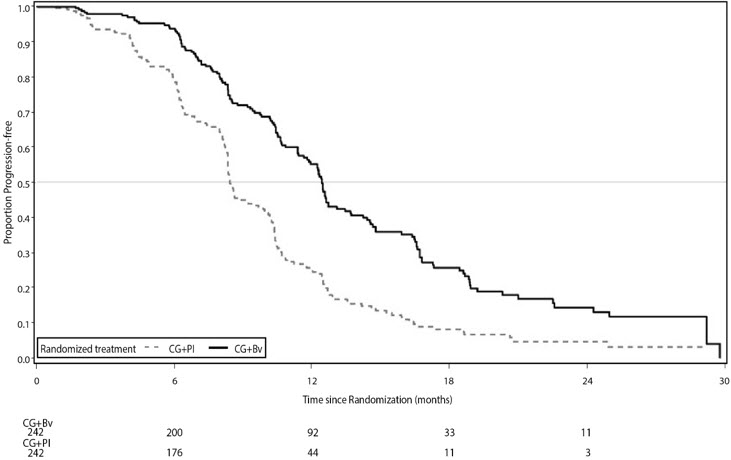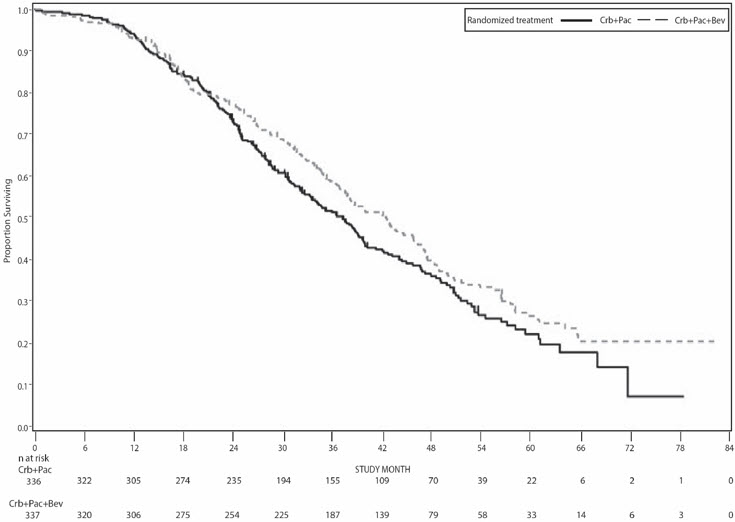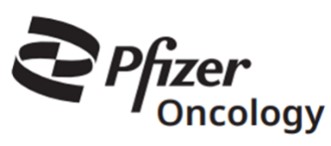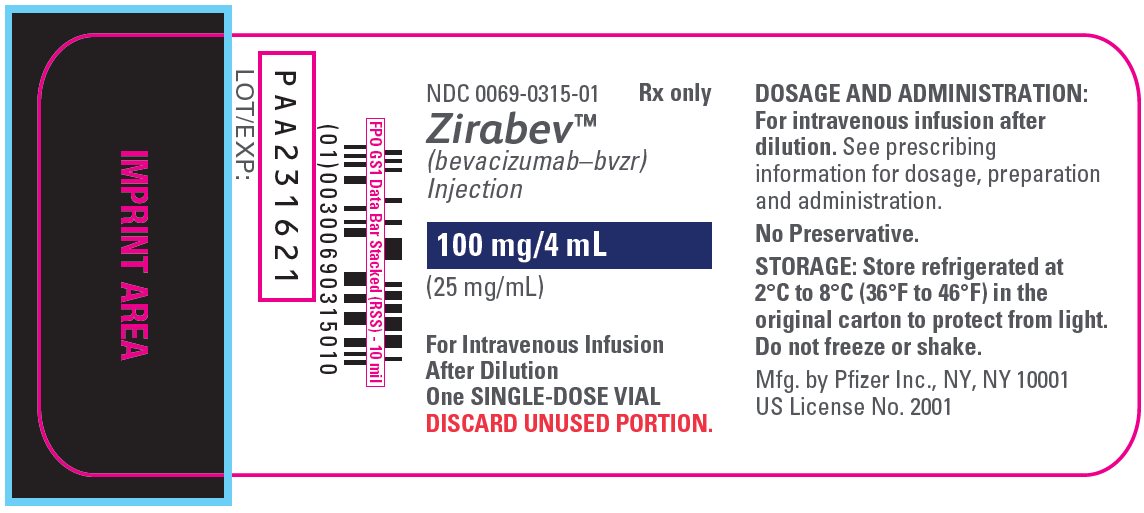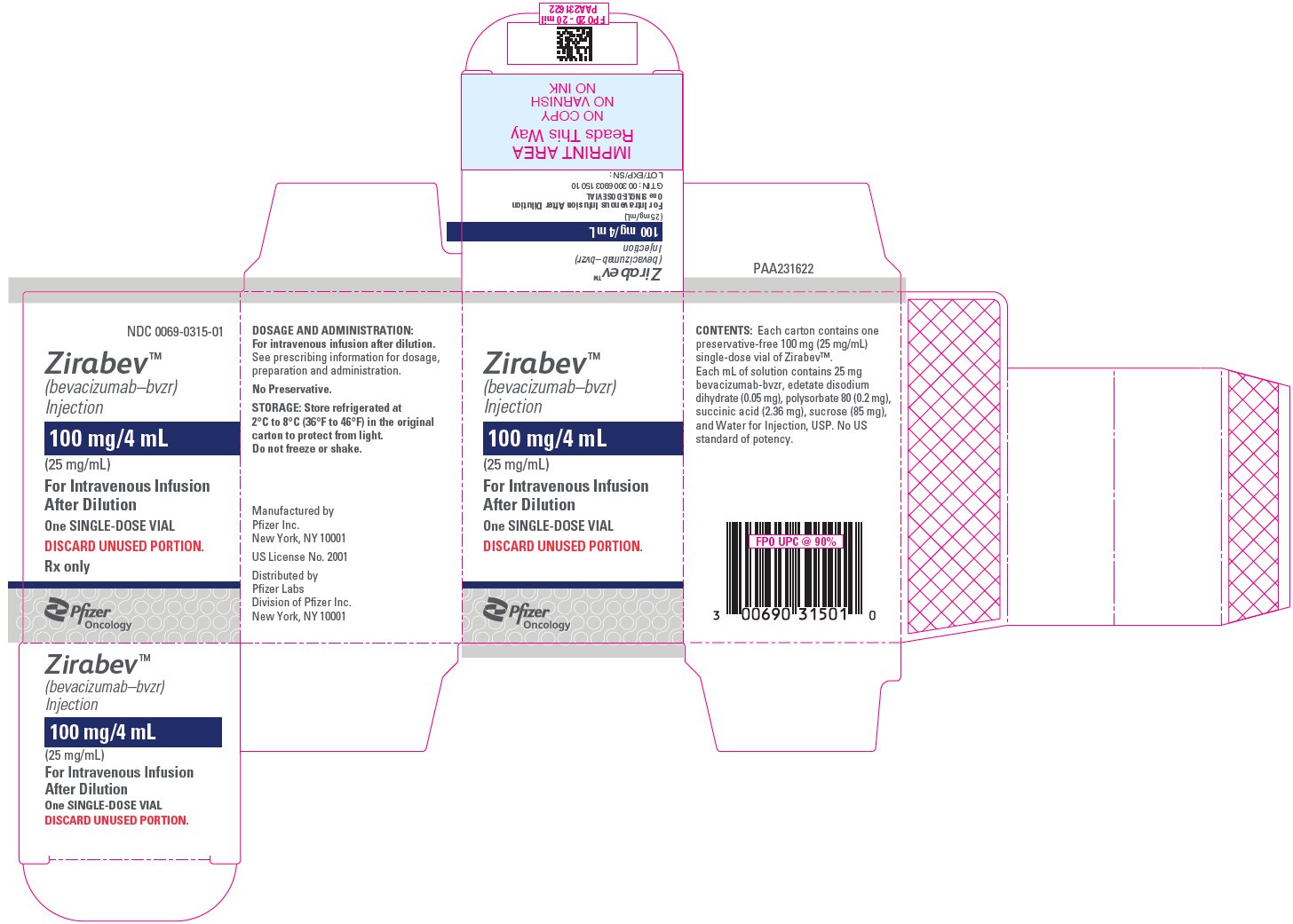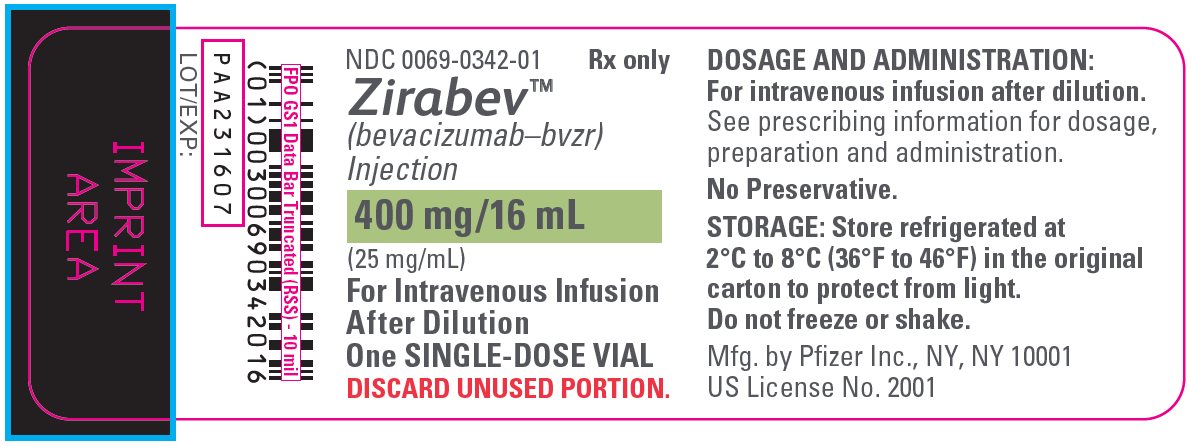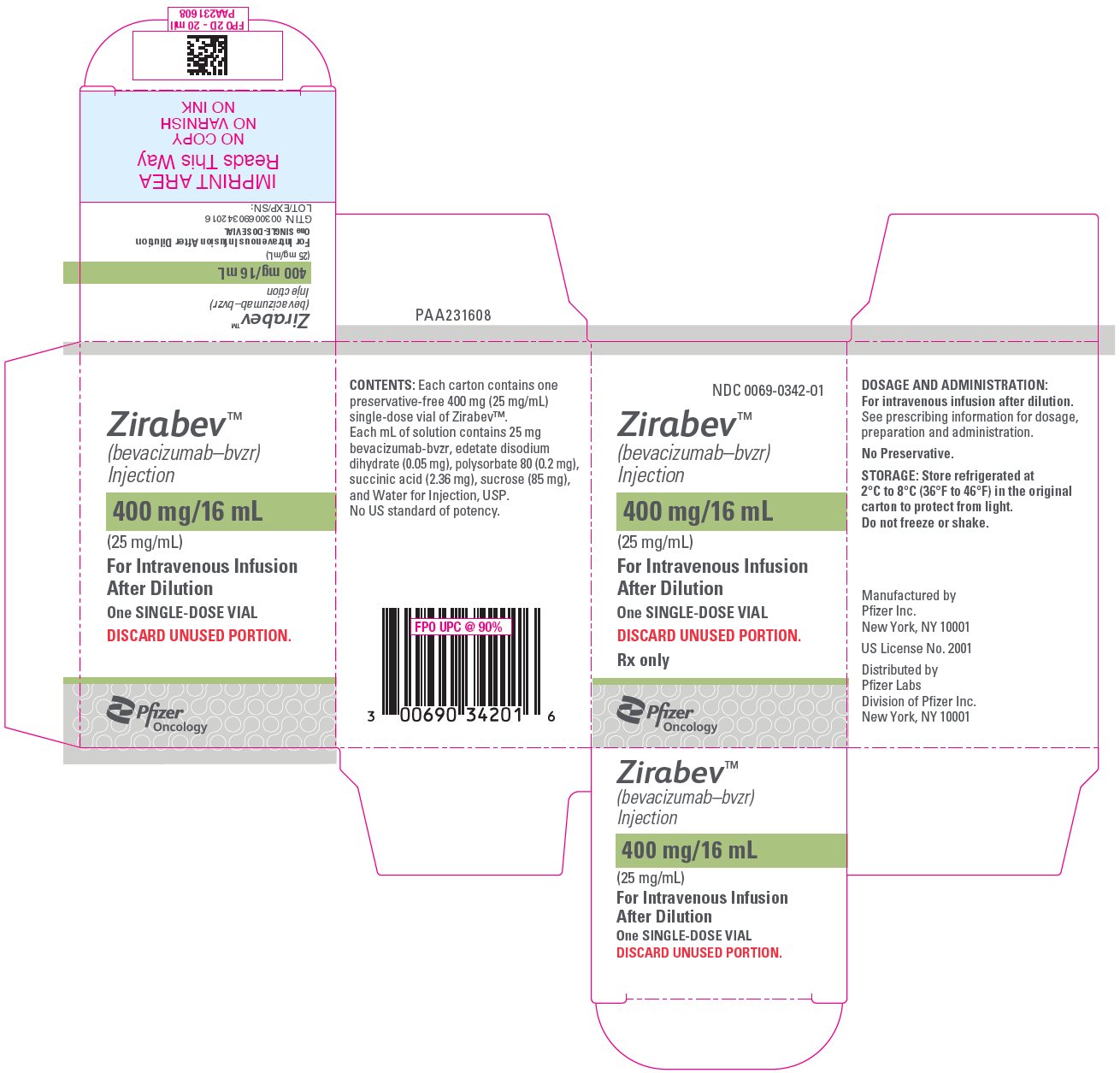 DRUG LABEL: Zirabev
NDC: 0069-0315 | Form: INJECTION, SOLUTION
Manufacturer: Pfizer Laboratories Div Pfizer Inc
Category: prescription | Type: HUMAN PRESCRIPTION DRUG LABEL
Date: 20250805

ACTIVE INGREDIENTS: BEVACIZUMAB 100 mg/4 mL
INACTIVE INGREDIENTS: EDETATE DISODIUM 0.2 mg/4 mL; POLYSORBATE 80 0.8 mg/4 mL; SUCCINIC ACID 9.4 mg/4 mL; SUCROSE 340 mg/4 mL; WATER

HIGHLIGHTS OF PRESCRIBING INFORMATION

These highlights do not include all the information needed to use ZIRABEV safely and effectively. See full prescribing information for ZIRABEV.
ZIRABEV™ (bevacizumab-bvzr) injection, for intravenous use
Initial U.S. Approval: 2019
ZIRABEV (bevacizumab-bvzr) is biosimilar [Biosimilar means that the biological product is approved based on data demonstrating that it is highly similar to an FDA-approved biological product, known as a reference product, and that there are no clinically meaningful differences between the biosimilar product and the reference product. Biosimilarity of ZIRABEV has been demonstrated for the condition(s) of use (e.g. indication(s), dosing regimen(s)), strength(s), dosage form(s), and route(s) of administration described in its Full Prescribing Information.] to AVASTIN (bevacizumab).

RECENT MAJOR CHANGES

Dosage and Administration, Preparation and Administration (2.9) | 8/2024

1 INDICATIONS AND USAGE

ZIRABEV is a vascular endothelial growth factor inhibitor indicated for the treatment of:

- Metastatic colorectal cancer, in combination with intravenous fluorouracil-based chemotherapy for first- or second-line treatment. (1.1)
- Metastatic colorectal cancer, in combination with fluoropyrimidine-irinotecan- or fluoropyrimidine-oxaliplatin-based chemotherapy for second-line treatment in patients who have progressed on a first-line bevacizumab product-containing regimen. (1.1)

Limitations of Use: ZIRABEV is not indicated for adjuvant treatment of colon cancer. (1.1)

- Unresectable, locally advanced, recurrent or metastatic non-squamous non-small cell lung cancer, in combination with carboplatin and paclitaxel for first-line treatment. (1.2)
- Recurrent glioblastoma in adults. (1.3)
- Metastatic renal cell carcinoma in combination with interferon alfa. (1.4)
- Persistent, recurrent, or metastatic cervical cancer, in combination with paclitaxel and cisplatin or paclitaxel and topotecan. (1.5)
- Epithelial ovarian, fallopian tube, or primary peritoneal cancer:
  - in combination with carboplatin and paclitaxel, followed by ZIRABEV as a single agent, for stage III or IV disease following initial surgical resection. (1.6)
  - in combination with paclitaxel, pegylated liposomal doxorubicin, or topotecan for platinum-resistant recurrent disease who received no more than 2 prior chemotherapy regimens. (1.6)
  - in combination with carboplatin and paclitaxel or carboplatin and gemcitabine, followed by ZIRABEV as a single agent, for platinum-sensitive recurrent disease. (1.6)

2 DOSAGE AND ADMINISTRATION

Withhold for at least 28 days prior to elective surgery. Do not administer ZIRABEV for 28 days following major surgery and until adequate wound healing. (2.1)

Metastatic colorectal cancer. (2.2)

- 5 mg/kg every 2 weeks with bolus-IFL.
- 10 mg/kg every 2 weeks with FOLFOX4.
- 5 mg/ kg every 2 weeks or 7.5 mg/kg every 3 weeks with fluoropyrimidine-irinotecan- or fluoropyrimidine-oxaliplatin based chemotherapy after progression on a first-line bevacizumab product containing regimen.

First-line non−squamous non−small cell lung cancer. (2.3)

- 15 mg/kg every 3 weeks with carboplatin and paclitaxel.

Recurrent glioblastoma. (2.4)

- 10 mg/kg every 2 weeks.

Metastatic renal cell carcinoma. (2.5)

- 10 mg/kg every 2 weeks with interferon alfa.

Persistent, recurrent, or metastatic cervical cancer. (2.6)

- 15 mg/kg every 3 weeks with paclitaxel and cisplatin or paclitaxel and topotecan.

Stage III or IV epithelial ovarian, fallopian tube or primary peritoneal cancer following initial surgical resection. (2.7)

- 15 mg/kg every 3 weeks with carboplatin and paclitaxel for up to 6 cycles, followed by 15 mg/kg every 3 weeks as a single agent, for a total of up to 22 cycles.

Platinum-resistant recurrent epithelial ovarian, fallopian tube or primary peritoneal cancer. (2.7)

- 10 mg/kg every 2 weeks with paclitaxel, pegylated liposomal doxorubicin, or topotecan given every week.
- 15 mg/kg every 3 weeks with topotecan given every 3 weeks

Platinum-sensitive recurrent epithelial ovarian, fallopian tube, or primary peritoneal cancer. (2.7)

- 15 mg/kg every 3 weeks with carboplatin and paclitaxel for 6–8 cycles, followed by 15 mg/kg every 3 weeks as a single agent.
- 15 mg/kg every 3 weeks with carboplatin and gemcitabine for 6–10 cycles, followed by 15 mg/kg every 3 weeks as a single agent.

Administer as an intravenous infusion after dilution. See full Prescribing Information for preparation and administration instructions and dosage modifications for adverse reactions. (2.8, 2.9)

3 DOSAGE FORMS AND STRENGTHS

Injection: 100 mg/4 mL (25 mg/mL) or 400 mg/16 mL (25 mg/mL) in a single-dose vial. (3)

4 CONTRAINDICATIONS

None (4)

5 WARNINGS AND PRECAUTIONS

- Gastrointestinal Perforations and Fistula: Discontinue for gastrointestinal perforations, tracheoesophageal fistula, grade 4 fistula, or fistula formation involving any organ. (5.1)
- Surgery and Wound Healing Complications: In patients who experience wound healing complications during ZIRABEV treatment, withhold ZIRABEV until adequate wound healing. Withhold for at least 28 days prior to elective surgery. Do not administer ZIRABEV for at least 28 days following a major surgery, and until adequate wound healing. The safety of resumption of bevacizumab products after resolution of wound healing complication has not been established. Discontinue for wound healing complications of necrotizing fasciitis. (5.2)
- Hemorrhage: Severe or fatal hemorrhages have occurred. Do not administer for recent hemoptysis. Discontinue for Grade 3–4 hemorrhage. (5.3)
- Arterial Thromboembolic Events (ATE): Discontinue for severe ATE. (5.4)
- Venous Thromboembolic Events (VTE): Discontinue for Grade 4 VTE. (5.5)
- Hypertension: Monitor blood pressure and treat hypertension. Withhold if not medically controlled; resume once controlled. Discontinue for hypertensive crisis or hypertensive encephalopathy. (5.6)
- Posterior Reversible Encephalopathy Syndrome (PRES): Discontinue. (5.7)
- Renal Injury and Proteinuria: Monitor urine protein. Discontinue for nephrotic syndrome. Withhold until less than 2 grams of protein in urine. (5.8)
- Infusion–Related Reactions: Decrease rate for infusion-related reactions. Discontinue for severe infusion-related reactions and administer medical therapy. (5.9)
- Embryo-Fetal Toxicity: May cause fetal harm. Advise females of potential risk to fetus and need for use of effective contraception. (5.10, 8.1, 8.3)
- Ovarian Failure: Advise females of the potential risk. (5.11, 8.3)
- Congestive Heart Failure (CHF): Discontinue ZIRABEV in patients who develop CHF. (5.12)

6 ADVERSE REACTIONS

Most common adverse reactions incidence (incidence >10%) are epistaxis, headache, hypertension, rhinitis, proteinuria, taste alteration, dry skin, hemorrhage, lacrimation disorder, back pain and exfoliative dermatitis. (6.1)

To report SUSPECTED ADVERSE REACTIONS, contact Pfizer Inc. at 1-800-438-1985 and https://www.pfizer.com or FDA at 1-800-FDA-1088 or www.fda.gov/medwatch.

8 USE IN SPECIFIC POPULATIONS

Lactation: Advise not to breastfeed. (8.2)

FULL PRESCRIBING INFORMATION

1 INDICATIONS AND USAGE

1.1 Metastatic Colorectal Cancer

ZIRABEV, in combination with intravenous fluorouracil-based chemotherapy, is indicated for the first- or second-line treatment of patients with metastatic colorectal cancer (mCRC).

ZIRABEV, in combination with fluoropyrimidine-irinotecan- or fluoropyrimidine-oxaliplatin-based chemotherapy, is indicated for the second-line treatment of patients with mCRC who have progressed on a first-line bevacizumab product-containing regimen.

Limitations of Use: ZIRABEV is not indicated for adjuvant treatment of colon cancer [see Clinical Studies (14.2)].

1.2 First-Line Non-Squamous Non-Small Cell Lung Cancer

ZIRABEV, in combination with carboplatin and paclitaxel, is indicated for the first-line treatment of patients with unresectable, locally advanced, recurrent or metastatic non–squamous non–small cell lung cancer (NSCLC).

1.3 Recurrent Glioblastoma

ZIRABEV is indicated for the treatment of recurrent glioblastoma (GBM) in adults.

1.4 Metastatic Renal Cell Carcinoma

ZIRABEV, in combination with interferon alfa, is indicated for the treatment of metastatic renal cell carcinoma (mRCC).

1.5 Persistent, Recurrent, or Metastatic Cervical Cancer

ZIRABEV, in combination with paclitaxel and cisplatin or paclitaxel and topotecan, is indicated for the treatment of patients with persistent, recurrent, or metastatic cervical cancer.

1.6 Epithelial Ovarian, Fallopian Tube, or Primary Peritoneal Cancer

ZIRABEV, in combination with carboplatin and paclitaxel, followed by ZIRABEV as a single agent, is indicated for the treatment of patients with stage III or IV epithelial ovarian, fallopian tube, or primary peritoneal cancer following initial surgical resection.

ZIRABEV, in combination with paclitaxel, pegylated liposomal doxorubicin, or topotecan, is indicated for the treatment of patients with platinum-resistant recurrent epithelial ovarian, fallopian tube, or primary peritoneal cancer who received no more than 2 prior chemotherapy regimens.

ZIRABEV, in combination with carboplatin and paclitaxel, or with carboplatin and gemcitabine, followed by ZIRABEV as a single agent, is indicated for the treatment of patients with platinum-sensitive recurrent epithelial ovarian, fallopian tube, or primary peritoneal cancer.

2 DOSAGE AND ADMINISTRATION

2.1 Important Administration Information

Withhold for at least 28 days prior to elective surgery. Do not administer ZIRABEV until at least 28 days following major surgery and until adequate wound healing.

2.2 Metastatic Colorectal Cancer

The recommended dosage when ZIRABEV is administered in combination with intravenous fluorouracil-based chemotherapy is:

- 5 mg/kg intravenously every 2 weeks in combination with bolus-IFL.
- 10 mg/kg intravenously every 2 weeks in combination with FOLFOX4.
- 5 mg/kg intravenously every 2 weeks or 7.5 mg/kg intravenously every 3 weeks in combination with fluoropyrimidine-irinotecan- or fluoropyrimidine-oxaliplatin-based chemotherapy in patients who have progressed on a first-line bevacizumab product-containing regimen.

2.3 First-Line Non-Squamous Non-Small Cell Lung Cancer

The recommended dosage is 15 mg/kg intravenously every 3 weeks in combination with carboplatin and paclitaxel.

2.4 Recurrent Glioblastoma

The recommended dosage is 10 mg/kg intravenously every 2 weeks.

2.5 Metastatic Renal Cell Carcinoma

The recommended dosage is 10 mg/kg intravenously every 2 weeks in combination with interferon alfa.

2.6 Persistent, Recurrent, or Metastatic Cervical Cancer

The recommended dosage is 15 mg/kg intravenously every 3 weeks in combination with paclitaxel and cisplatin or in combination with paclitaxel and topotecan.

2.7 Epithelial Ovarian, Fallopian Tube, or Primary Peritoneal Cancer

Stage III or IV Disease Following Initial Surgical Resection

The recommended dosage is 15 mg/kg intravenously every 3 weeks in combination with carboplatin and paclitaxel for up to 6 cycles, followed by ZIRABEV 15 mg/kg every 3 weeks as a single agent for a total of up to 22 cycles or until disease progression, whichever occurs earlier.

Recurrent Disease

Platinum Resistant

The recommended dosage is 10 mg/kg intravenously every 2 weeks in combination with paclitaxel, pegylated liposomal doxorubicin, or topotecan (every week).

The recommended dosage is 15 mg/kg intravenously every 3 weeks in combination with topotecan (every 3 weeks).

Platinum Sensitive

The recommended dosage is 15 mg/kg intravenously every 3 weeks, in combination with carboplatin and paclitaxel for 6 to 8 cycles, followed by ZIRABEV 15 mg/kg every 3 weeks as a single agent until disease progression.

The recommended dosage is 15 mg/kg intravenously every 3 weeks, in combination with carboplatin and gemcitabine for 6 to 10 cycles, followed by ZIRABEV 15 mg/kg every 3 weeks as a single agent until disease progression.

2.8 Dosage Modifications for Adverse Reactions

Table 1 describes dosage modifications for specific adverse reactions. No dose reductions for ZIRABEV are recommended.

Table 1: Dosage Modifications for Adverse Reactions
Adverse Reaction | Severity | Dosage Modification
Gastrointestinal Perforations and Fistulae [see Warnings and Precautions (5.1)]. | - Gastrointestinal perforation, any grade - Tracheoesophageal fistula, any grade - Fistula, Grade 4 - Fistula formation involving any internal organ | Discontinue ZIRABEV
Wound Healing Complications [see Warnings and Precautions (5.2)]. | - Any | Withhold ZIRABEV until adequate wound healing. The safety of resumption of bevacizumab products after resolution of wound healing complications has not been established.
Wound Healing Complications [see Warnings and Precautions (5.2)]. | - Necrotizing fasciitis | Discontinue ZIRABEV
Hemorrhage [see Warnings and Precautions (5.3)]. | - Grade 3 or 4 | Discontinue ZIRABEV
Hemorrhage [see Warnings and Precautions (5.3)]. | - Recent history of hemoptysis of 1/2 teaspoon (2.5 mL) or more | Withhold ZIRABEV
Thromboembolic Events [see Warnings and Precautions (5.4, 5.5)]. | - Arterial thromboembolism, severe | Discontinue ZIRABEV
Thromboembolic Events [see Warnings and Precautions (5.4, 5.5)]. | - Venous thromboembolism, Grade 4 | Discontinue ZIRABEV
Hypertension [see Warnings and Precautions (5.6)]. | - Hypertensive crisis - Hypertensive encephalopathy | Discontinue ZIRABEV
Hypertension [see Warnings and Precautions (5.6)]. | - Hypertension, severe | Withhold ZIRABEV if not controlled with medical management; resume once controlled
Posterior Reversible Encephalopathy Syndrome (PRES) [see Warnings and Precautions (5.7)]. | - Any | Discontinue ZIRABEV
Renal Injury and Proteinuria [see Warnings and Precautions (5.8)]. | - Nephrotic syndrome | Discontinue ZIRABEV
Renal Injury and Proteinuria [see Warnings and Precautions (5.8)]. | - Proteinuria greater than or equal to 2 grams per 24 hours in absence of nephrotic syndrome | Withhold ZIRABEV until proteinuria less than 2 grams per 24 hours
Infusion-Related Reactions [see Warnings and Precautions (5.9)]. | - Severe | Discontinue ZIRABEV
Infusion-Related Reactions [see Warnings and Precautions (5.9)]. | - Clinically significant | Interrupt infusion; resume at a decreased rate of infusion after symptoms resolve
Infusion-Related Reactions [see Warnings and Precautions (5.9)]. | - Mild, clinically insignificant | Decrease infusion rate
Congestive Heart Failure [see Warnings and Precautions (5.12)]. | - Any | Discontinue ZIRABEV

2.9 Preparation and Administration

Preparation

- Use appropriate aseptic technique.
- Use sterile needle and syringe to prepare ZIRABEV.
- Visually inspect vial for particulate matter and discoloration prior to preparation for administration. Discard vial if solution is cloudy, discolored, or contains particulate matter.
- Withdraw necessary amount of ZIRABEV and dilute in a total volume of 100 mL of 0.9% Sodium Chloride Injection, USP. DO NOT ADMINISTER OR MIX WITH DEXTROSE SOLUTION.
- Discard any unused portion left in a vial, as the product contains no preservatives.
- Diluted ZIRABEV solution may be stored at 2°C to 8°C (36°F to 46°F) for up to 16 days, if not used immediately.
- No incompatibilities between ZIRABEV and polyvinylchloride or polyolefin bags have been observed.

Administration

- Administer as an intravenous infusion.
- First infusion: Administer infusion over 90 minutes.
- Subsequent infusions: Administer second infusion over 60 minutes if first infusion is tolerated. Administer all subsequent infusions over 30 minutes if second infusion over 60 minutes is tolerated.

3 DOSAGE FORMS AND STRENGTHS

Injection: 100 mg/4 mL (25 mg/mL) or 400 mg/16 mL (25 mg/mL) clear to slightly opalescent, colorless to pale brown solution in a single-dose vial

4 CONTRAINDICATIONS

None.

5 WARNINGS AND PRECAUTIONS

5.1 Gastrointestinal Perforations and Fistulae

Serious and sometimes fatal gastrointestinal perforation occurred at a higher incidence in patients receiving bevacizumab products compared to patients receiving chemotherapy. The incidence ranged from 0.3% to 3% across clinical studies, with the highest incidence in patients with a history of prior pelvic radiation. Perforation can be complicated by intra-abdominal abscess, fistula formation, and the need for diverting ostomies. The majority of perforations occurred within 50 days of the first dose [see Adverse Reactions (6.1)].

Serious fistulae (including, tracheoesophageal, bronchopleural, biliary, vaginal, renal and bladder sites) occurred at a higher incidence in patients receiving bevacizumab products compared to patients receiving chemotherapy. The incidence ranged from <1% to 1.8% across clinical studies, with the highest incidence in patients with cervical cancer. The majority of fistulae occurred within 6 months of the first dose. Patients who develop a gastrointestinal vaginal fistula may also have a bowel obstruction and require surgical intervention, as well as a diverting ostomy.

Avoid ZIRABEV in patients with ovarian cancer who have evidence of recto-sigmoid involvement by pelvic examination or bowel involvement on CT scan or clinical symptoms of bowel obstruction. Discontinue in patients who develop gastrointestinal perforation, tracheoesophageal fistula or any Grade 4 fistula. Discontinue in patients with fistula formation involving any internal organ.

5.2 Surgery and Wound Healing Complications

In a controlled clinical study in which bevacizumab was not administered within 28 days of major surgical procedures, the incidence of wound healing complications, including serious and fatal complications, was 15% in patients with mCRC who underwent surgery while receiving bevacizumab and 4% in patients who did not receive bevacizumab. In a controlled clinical study in patients with relapsed or recurrent GBM, the incidence of wound healing events was 5% in patients who received bevacizumab and 0.7% in patients who did not receive bevacizumab [see Adverse Reactions (6.1)].

In patients who experience wound healing complications during ZIRABEV treatment, withhold ZIRABEV until adequate wound healing. Withhold for at least 28 days prior to elective surgery. Do not administer for at least 28 days following major surgery and until adequate wound healing. The safety of resumption of bevacizumab products after resolution of wound healing complications has not been established [see Dosage and Administration (2.7)].

Necrotizing fasciitis including fatal cases, has been reported in patients receiving bevacizumab usually secondary to wound healing complications, gastrointestinal perforation or fistula formation. Discontinue ZIRABEV in patients who develop necrotizing fasciitis.

5.3 Hemorrhage

Bevacizumab products can result in two distinct patterns of bleeding: minor hemorrhage, which is most commonly Grade 1 epistaxis, and serious hemorrhage, which in some cases has been fatal. Severe or fatal hemorrhage, including hemoptysis, gastrointestinal bleeding, hematemesis, CNS hemorrhage, epistaxis, and vaginal bleeding occurred up to 5-fold more frequently in patients receiving bevacizumab compared to patients receiving chemotherapy alone. Across clinical studies, the incidence of Grades 3–5 hemorrhagic events ranged from 0.4% to 7% in patients receiving bevacizumab [see Adverse Reactions (6.1)].

Serious or fatal pulmonary hemorrhage occurred in 31% of patients with squamous NSCLC and 4% of patients with non-squamous NSCLC receiving bevacizumab with chemotherapy compared to none of the patients receiving chemotherapy alone.

Do not administer ZIRABEV to patients with recent history of hemoptysis of 1/2 teaspoon or more of red blood. Discontinue in patients who develop a Grades 3–4 hemorrhage.

5.4 Arterial Thromboembolic Events

Serious, sometimes fatal, arterial thromboembolic events (ATE) including cerebral infarction, transient ischemic attacks, myocardial infarction, and angina, occurred at a higher incidence in patients receiving bevacizumab compared to patients receiving chemotherapy. Across clinical studies, the incidence of Grades 3–5 ATE was 5% in patients receiving bevacizumab with chemotherapy compared to ≤2% in patients receiving chemotherapy alone; the highest incidence occurred in patients with GBM. The risk of developing ATE was increased in patients with a history of arterial thromboembolism, diabetes, or ≥65 years [see Use in Specific Populations (8.5)].

Discontinue in patients who develop a severe ATE. The safety of reinitiating bevacizumab products after an ATE is resolved is not known.

5.5 Venous Thromboembolic Events

An increased risk of venous thromboembolic events (VTE) was observed across clinical studies [see Adverse Reactions (6.1)]. In Study GOG-0240, Grades 3–4 VTE occurred in 11% of patients receiving bevacizumab with chemotherapy compared with 5% of patients receiving chemotherapy alone. In EORTC 26101, the incidence of Grades 3–4 VTE was 5% in patients receiving bevacizumab with chemotherapy compared to 2% in patients receiving chemotherapy alone.

Discontinue ZIRABEV in patients with a Grade 4 VTE, including pulmonary embolism.

5.6 Hypertension

Severe hypertension occurred at a higher incidence in patients receiving bevacizumab products as compared to patients receiving chemotherapy alone. Across clinical studies, the incidence of Grades 3–4 hypertension ranged from 5% to 18%.

Monitor blood pressure every two to three weeks during treatment with ZIRABEV. Treat with appropriate anti-hypertensive therapy and monitor blood pressure regularly. Continue to monitor blood pressure at regular intervals in patients with ZIRABEV-induced or -exacerbated hypertension after discontinuing ZIRABEV. Withhold ZIRABEV in patients with severe hypertension that is not controlled with medical management; resume once controlled with medical management. Discontinue in patients who develop hypertensive crisis or hypertensive encephalopathy.

5.7 Posterior Reversible Encephalopathy Syndrome

Posterior reversible encephalopathy syndrome (PRES) was reported in <0.5% of patients across clinical studies. The onset of symptoms occurred from 16 hours to 1 year after the first dose. PRES is a neurological disorder which can present with headache, seizure, lethargy, confusion, blindness and other visual and neurologic disturbances. Mild to severe hypertension may be present. Magnetic resonance imaging is necessary to confirm the diagnosis of PRES.

Discontinue ZIRABEV in patients who develop PRES. Symptoms usually resolve or improve within days after discontinuing bevacizumab products, although some patients have experienced ongoing neurologic sequelae. The safety of reinitiating bevacizumab products in patients who developed PRES is not known.

5.8 Renal Injury and Proteinuria

The incidence and severity of proteinuria was higher in patients receiving bevacizumab as compared to patients receiving chemotherapy. Grade 3 (defined as urine dipstick 4+ or >3.5 grams of protein per 24 hours) to Grade 4 (defined as nephrotic syndrome) ranged from 0.7% to 7% in clinical studies.

The overall incidence of proteinuria (all grades) was only adequately assessed in Study BO17705, in which the incidence was 20%. Median onset of proteinuria was 5.6 months (15 days to 37 months) after initiating bevacizumab. Median time to resolution was 6.1 months (95% CI: 2.8, 11.3). Proteinuria did not resolve in 40% of patients after median follow-up of 11.2 months and required discontinuation of bevacizumab in 30% of the patients who developed proteinuria [see Adverse Reactions (6.1)].

In an exploratory, pooled analysis of patients from seven randomized clinical studies, 5% of patients receiving bevacizumab with chemotherapy experienced Grades 2–4 (defined as urine dipstick 2+ or greater or >1 gram of protein per 24 hours or nephrotic syndrome) proteinuria. Grades 2–4 proteinuria resolved in 74% of patients.

Bevacizumab was reinitiated in 42% of patients. Of the 113 patients who reinitiated bevacizumab, 48% experienced a second episode of Grades 2–4 proteinuria.

Nephrotic syndrome occurred in <1% of patients receiving bevacizumab across clinical studies, in some instances with fatal outcome. In a published case series, kidney biopsy of 6 patients with proteinuria showed findings consistent with thrombotic microangiopathy. Results of a retrospective analysis of 5805 patients who received bevacizumab with chemotherapy and 3713 patients who received chemotherapy alone, showed higher rates of elevated serum creatinine levels (between 1.5 to 1.9 times baseline levels) in patients who received bevacizumab. Serum creatinine levels did not return to baseline in approximately one-third of patients who received bevacizumab.

Monitor proteinuria by dipstick urine analysis for the development or worsening of proteinuria with serial urinalyses during ZIRABEV therapy. Patients with a 2+ or greater urine dipstick reading should undergo further assessment with a 24-hour urine collection. Withhold for proteinuria greater than or equal to 2 grams per 24 hours and resume when less than 2 grams per 24 hours. Discontinue in patients who develop nephrotic syndrome.

Data from a postmarketing safety study showed poor correlation between UPCR (Urine Protein/Creatinine Ratio) and 24-hour urine protein [Pearson Correlation 0.39 (95% CI: 0.17, 0.57)].

5.9 Infusion-Related Reactions

Infusion-related reactions reported across clinical studies and postmarketing experience include hypertension, hypertensive crises associated with neurologic signs and symptoms, wheezing, oxygen desaturation, Grade 3 hypersensitivity, anaphylactoid/anaphylactic reactions, chest pain, headaches, rigors, and diaphoresis. In clinical studies, infusion-related reactions with the first dose occurred in <3% of patients and severe reactions occurred in 0.4% of patients.

Decrease the rate of infusion for mild, clinically insignificant infusion-related reactions. Interrupt the infusion in patients with clinically significant infusion-related reactions and consider resuming at a slower rate following resolution. Discontinue in patients who develop a severe infusion-related reaction and administer appropriate medical therapy (e.g., epinephrine, corticosteroids, intravenous antihistamines, bronchodilators and/or oxygen).

5.10 Embryo-Fetal Toxicity

Based on its mechanism of action and findings from animal studies, bevacizumab products may cause fetal harm when administered to pregnant women. Congenital malformations were observed with the administration of bevacizumab to pregnant rabbits during organogenesis every 3 days at a dose as low as a clinical dose of 10 mg/kg.

Furthermore, animal models link angiogenesis and VEGF and VEGFR2 to critical aspects of female reproduction, embryo-fetal development, and postnatal development. Advise pregnant women of the potential risk to a fetus. Advise females of reproductive potential to use effective contraception during treatment with ZIRABEV and for 6 months after the last dose [see Use in Specific Populations (8.1, 8.3)].

5.11 Ovarian Failure

The incidence of ovarian failure was 34% vs. 2% in premenopausal women receiving bevacizumab with chemotherapy as compared to those receiving chemotherapy alone for adjuvant treatment of a solid tumor. After discontinuing bevacizumab, recovery of ovarian function at all time points during the post-treatment period was demonstrated in 22% of women receiving bevacizumab. Recovery of ovarian function is defined as resumption of menses, a positive serum β-HCG pregnancy test, or an FSH level <30 mIU/mL during the post-treatment period. Long-term effects of bevacizumab products on fertility are unknown. Inform females of reproductive potential of the risk of ovarian failure prior to initiating ZIRABEV [see Adverse Reactions (6.1), Use in Specific Populations (8.3)].

5.12 Congestive Heart Failure (CHF)

ZIRABEV is not indicated for use with anthracycline-based chemotherapy. The incidence of Grade ≥3 left ventricular dysfunction was 1% in patients receiving bevacizumab compared to 0.6% of patients receiving chemotherapy alone. Among patients who received prior anthracycline treatment, the rate of CHF was 4% for patients receiving bevacizumab with chemotherapy as compared to 0.6% for patients receiving chemotherapy alone.

In previously untreated patients with a hematological malignancy, the incidence of CHF and decline in left ventricular ejection fraction (LVEF) were increased in patients receiving bevacizumab with anthracycline-based chemotherapy compared to patients receiving placebo with the same chemotherapy regimen. The proportion of patients with a decline in LVEF from baseline of ≥20% or a decline from baseline of 10% to <50%, was 10% in patients receiving bevacizumab with chemotherapy compared to 5% in patients receiving chemotherapy alone. Time to onset of left-ventricular dysfunction or CHF was 1 to 6 months after the first dose in at least 85% of the patients and was resolved in 62% of the patients who developed CHF in the bevacizumab arm compared to 82% in the placebo arm. Discontinue ZIRABEV in patients who develop CHF.

6 ADVERSE REACTIONS

The following clinically significant adverse reactions are described elsewhere in the labeling:

- Gastrointestinal Perforations and Fistulae [see Warnings and Precautions (5.1)].
- Surgery and Wound Healing Complications [see Warnings and Precautions (5.2)].
- Hemorrhage [see Warnings and Precautions (5.3)].
- Arterial Thromboembolic Events [see Warnings and Precautions (5.4)].
- Venous Thromboembolic Events [see Warnings and Precautions (5.5)].
- Hypertension [see Warnings and Precautions (5.6)].
- Posterior Reversible Encephalopathy Syndrome [see Warnings and Precautions (5.7)].
- Renal Injury and Proteinuria [see Warnings and Precautions (5.8)].
- Infusion-Related Reactions [see Warnings and Precautions (5.9)].
- Ovarian Failure [see Warnings and Precautions (5.11)].
- Congestive Heart Failure [see Warnings and Precautions (5.12)].

6.1 Clinical Trials Experience

Because clinical studies are conducted under widely varying conditions, adverse reaction rates observed in the clinical studies of a drug cannot be directly compared to rates in the clinical studies of another drug and may not reflect the rates observed in practice.

The safety data in Warnings and Precautions and described below reflect exposure to bevacizumab in 4463 patients including those with mCRC (AVF2107g, E3200), non-squamous NSCLC (E4599), GBM (EORTC 26101), mRCC (BO17705), cervical cancer (GOG-0240), epithelial ovarian, fallopian tube, or primary peritoneal cancer (MO22224, AVF4095, GOG-0213, and GOG-0218) or another cancer at the recommended dose and schedule for a median of 6 to 23 doses. The most common adverse reactions observed in patients receiving bevacizumab as a single agent or in combination with other anti-cancer therapies at a rate >10% were epistaxis, headache, hypertension, rhinitis, proteinuria, taste alteration, dry skin, hemorrhage, lacrimation disorder, back pain, and exfoliative dermatitis.

Across clinical studies, bevacizumab was discontinued in 8% to 22% of patients because of adverse reactions [see Clinical Studies (14)].

Metastatic Colorectal Cancer

In Combination with bolus IFL

The safety of bevacizumab was evaluated in 392 patients who received at least one dose of bevacizumab in a double-blind, active-controlled study (AVF2107g), which compared bevacizumab (5 mg/kg every 2 weeks) with bolus-IFL to placebo with bolus IFL in patients with mCRC [see Clinical Studies (14.1)]. Patients were randomized (1:1:1) to placebo with bolus IFL, bevacizumab with bolus IFL, or bevacizumab with fluorouracil and leucovorin. The demographics of the safety population were similar to the demographics of the efficacy population. All Grades 3–4 adverse reactions and selected Grades 1–2 adverse reactions (i.e., hypertension, proteinuria, thromboembolic events) were collected in the entire study population. Adverse reactions are presented in Table 2.

Table 2: Grades 3–4 Adverse Reactions Occurring at Higher Incidence (≥2%) in Patients Receiving Bevacizumab vs. Placebo in Study AVF2107g
Adverse Reaction [NCI-CTC version 3] | Bevacizumab with IFL (N=392) | Placebo with IFL (N=396)
Hematology
Leukopenia | 37% | 31%
Neutropenia | 21% | 14%
Gastrointestinal
Diarrhea | 34% | 25%
Abdominal pain | 8% | 5%
Constipation | 4% | 2%
Vascular
Hypertension | 12% | 2%
Deep vein thrombosis | 9% | 5%
Intra-abdominal thrombosis | 3% | 1%
Syncope | 3% | 1%
General
Asthenia | 10% | 7%
Pain | 8% | 5%

In Combination with FOLFOX4

The safety of bevacizumab was evaluated in 521 patients in an open-label, active-controlled study (E3200) in patients who were previously treated with irinotecan and fluorouracil for initial therapy for mCRC. Patients were randomized (1:1:1) to FOLFOX4, bevacizumab (10 mg/kg every 2 weeks prior to FOLFOX4 on Day 1) with FOLFOX4, or bevacizumab alone (10 mg/kg every 2 weeks). Bevacizumab was continued until disease progression or unacceptable toxicity. The demographics of the safety population were similar to the demographics of the efficacy population.

Selected Grades 3–5 non-hematologic and Grades 4–5 hematologic occurring at a higher incidence (≥2%) in patients receiving bevacizumab with FOLFOX4 compared to FOLFOX4 alone were fatigue (19% vs. 13%), diarrhea (18% vs. 13%), sensory neuropathy (17% vs. 9%), nausea (12% vs. 5%), vomiting (11% vs. 4%), dehydration (10% vs. 5%), hypertension (9% vs. 2%), abdominal pain (8% vs. 5%), hemorrhage (5% vs. 1%), other neurological (5% vs. 3%), ileus (4% vs. 1%) and headache (3% vs. 0%). These data are likely to under-estimate the true adverse reaction rates due to the reporting mechanisms.

First-Line Non-Squamous Non-Small Cell Lung Cancer

The safety of bevacizumab was evaluated as first-line treatment in 422 patients with unresectable NSCLC who received at least one dose of bevacizumab in an active-controlled, open-label, multicenter trial (E4599) [see Clinical Studies (14.3)]. Chemotherapy-naïve patients with locally advanced, metastatic or recurrent non–squamous NSCLC were randomized (1:1) to receive six 21-day cycles of paclitaxel and carboplatin with or without bevacizumab (15 mg/kg every 3 weeks). After completion or upon discontinuation of chemotherapy, patients randomized to receive bevacizumab continued to receive bevacizumab alone until disease progression or until unacceptable toxicity. The trial excluded patients with predominant squamous histology (mixed cell type tumors only), CNS metastasis, gross hemoptysis (1/2 teaspoon or more of red blood), unstable angina, or receiving therapeutic anticoagulation. The demographics of the safety population were similar to the demographics of the efficacy population.

Only Grades 3–5 non-hematologic and Grades 4–5 hematologic adverse reactions were collected. Grades 3–5 non-hematologic and Grades 4–5 hematologic adverse reactions occurring at a higher incidence (≥2%) in patients receiving bevacizumab with paclitaxel and carboplatin compared with patients receiving chemotherapy alone were neutropenia (27% vs. 17%), fatigue (16% vs. 13%), hypertension (8% vs. 0.7%), infection without neutropenia (7% vs. 3%), venous thromboembolism (5% vs. 3%), febrile neutropenia (5% vs. 2%), pneumonitis/pulmonary infiltrates (5% vs. 3%), infection with Grade 3 or 4 neutropenia (4% vs. 2%), hyponatremia (4% vs. 1%), headache (3% vs. 1%) and proteinuria (3% vs. 0%).

Recurrent Glioblastoma

The safety of bevacizumab was evaluated in a multicenter, randomized, open-label study (EORTC 26101) in patients with recurrent GBM following radiotherapy and temozolomide of whom 278 patients received at least one dose of bevacizumab and are considered safety evaluable [see Clinical Studies (14.4)]. Patients were randomized (2:1) to receive bevacizumab (10 mg/kg every 2 weeks) with lomustine or lomustine alone until disease progression or unacceptable toxicity. The demographics of the safety population were similar to the demographics of the efficacy population. In the bevacizumab with lomustine arm, 22% of patients discontinued treatment due to adverse reactions compared with 10% of patients in the lomustine arm. In patients receiving bevacizumab with lomustine, the adverse reaction profile was similar to that observed in other approved indications.

Metastatic Renal Cell Carcinoma

The safety of bevacizumab was evaluated in 337 patients who received at least one dose of bevacizumab in a multicenter, double-blind study (BO17705) in patients with mRCC. Patients who had undergone a nephrectomy were randomized (1:1) to receive either bevacizumab (10 mg/kg every 2 weeks) or placebo with interferon alfa [see Clinical Studies (14.5)]. Patients were treated until disease progression or unacceptable toxicity. The demographics of the safety population were similar to the demographics of the efficacy population.

Grades 3–5 adverse reactions occurring at a higher incidence (>2%) were fatigue (13% vs. 8%), asthenia (10% vs. 7%), proteinuria (7% vs. 0%), hypertension (6% vs. 1%; including hypertension and hypertensive crisis), and hemorrhage (3% vs. 0.3%; including epistaxis, small intestinal hemorrhage, aneurysm ruptured, gastric ulcer hemorrhage, gingival bleeding, hemoptysis, hemorrhage intracranial, large intestinal hemorrhage, respiratory tract hemorrhage, and traumatic hematoma). Adverse reactions are presented in Table 3.

Table 3: Grades 1–5 Adverse Reactions Occurring at Higher Incidence (≥5%) of Patients Receiving Bevacizumab vs. Placebo with Interferon Alfa in Study BO17705
Adverse Reaction [NCI-CTC version 3] | Bevacizumab with Interferon Alfa (N=337) | Placebo with Interferon Alfa (N=304)
Metabolism and nutrition
Decreased appetite | 36% | 31%
Weight loss | 20% | 15%
General
Fatigue | 33% | 27%
Vascular
Hypertension | 28% | 9%
Respiratory, thoracic and mediastinal
Epistaxis | 27% | 4%
Dysphonia | 5% | 0%
Nervous system
Headache | 24% | 16%
Gastrointestinal
Diarrhea | 21% | 16%
Renal and urinary
Proteinuria | 20% | 3%
Musculoskeletal and connective tissue
Myalgia | 19% | 14%
Back pain | 12% | 6%

The following adverse reactions were reported at a 5-fold greater incidence in patients receiving bevacizumab with interferon-alfa compared to patients receiving placebo with interferon-alfa and not represented in Table 3: gingival bleeding (13 patients vs. 1 patient); rhinitis (9 vs. 0); blurred vision (8 vs. 0); gingivitis (8 vs. 1); gastroesophageal reflux disease (8 vs. 1); tinnitus (7 vs. 1); tooth abscess (7 vs. 0); mouth ulceration (6 vs. 0); acne (5 vs. 0); deafness (5 vs. 0); gastritis (5 vs. 0); gingival pain (5 vs. 0) and pulmonary embolism (5 vs. 1).

Persistent, Recurrent, or Metastatic Cervical Cancer

The safety of bevacizumab was evaluated in 218 patients who received at least one dose of bevacizumab in a multicenter study (GOG-0240) in patients with persistent, recurrent, or metastatic cervical cancer [see Clinical Studies (14.6)]. Patients were randomized (1:1:1:1) to receive paclitaxel and cisplatin with or without bevacizumab (15 mg/kg every 3 weeks), or paclitaxel and topotecan with or without bevacizumab (15 mg/kg every 3 weeks). The demographics of the safety population were similar to the demographics of the efficacy population.

Grades 3–4 adverse reactions occurring at a higher incidence (≥2%) in 218 patients receiving bevacizumab with chemotherapy compared to 222 patients receiving chemotherapy alone were abdominal pain (12% vs. 10%), hypertension (11% vs. 0.5%), thrombosis (8% vs. 3%), diarrhea (6% vs. 3%), anal fistula (4% vs. 0%), proctalgia (3% vs. 0%), urinary tract infection (8% vs. 6%), cellulitis (3% vs. 0.5%), fatigue (14% vs. 10%), hypokalemia (7% vs. 4%), hyponatremia (4% vs. 1%), dehydration (4% vs. 0.5%), neutropenia (8% vs. 4%), lymphopenia (6% vs. 3%), back pain (6% vs. 3%), and pelvic pain (6% vs. 1%). Adverse reactions are presented in Table 4.

Table 4: Grades 1–4 Adverse Reactions Occurring at Higher Incidence (≥5%) in Patients Receiving Bevacizumab with Chemotherapy vs. Chemotherapy Alone in Study GOG-0240
Adverse Reaction [NCI-CTC version 3] | Bevacizumab with Chemotherapy (N=218) | Chemotherapy (N=222)
General
Fatigue | 80% | 75%
Peripheral edema | 15% | 22%
Metabolism and nutrition
Decreased appetite | 34% | 26%
Hyperglycemia | 26% | 19%
Hypomagnesemia | 24% | 15%
Weight loss | 21% | 7%
Hyponatremia | 19% | 10%
Hypoalbuminemia | 16% | 11%
Vascular
Hypertension | 29% | 6%
Thrombosis | 10% | 3%
Infections
Urinary tract infection | 22% | 14%
Infection | 10% | 5%
Nervous system
Headache | 22% | 13%
Dysarthria | 8% | 1%
Psychiatric
Anxiety | 17% | 10%
Respiratory, thoracic and mediastinal
Epistaxis | 17% | 1%
Renal and urinary
Increased blood creatinine | 16% | 10%
Proteinuria | 10% | 3%
Gastrointestinal
Stomatitis | 15% | 10%
Proctalgia | 6% | 1%
Anal fistula | 6% | 0%
Reproductive system and breast
Pelvic pain | 14% | 8%
Hematology
Neutropenia | 12% | 6%
Lymphopenia | 12% | 5%

Epithelial Ovarian, Fallopian Tube, or Primary Peritoneal Cancer

Stage III or IV Following Initial Surgical Resection

The safety of bevacizumab was evaluated in GOG-0218, a multicenter, randomized, double-blind, placebo-controlled, three arm study, which evaluated the addition of bevacizumab to carboplatin and paclitaxel for the treatment of patients with stage III or IV epithelial ovarian, fallopian tube, or primary peritoneal cancer following initial surgical resection [see Clinical Studies (14.7)]. Patients were randomized (1:1:1) to carboplatin and paclitaxel without bevacizumab (CPP), carboplatin and paclitaxel with bevacizumab for up to six cycles (CPB15), or carboplatin and paclitaxel with bevacizumab for six cycles followed by bevacizumab as a single agent for up to 16 additional doses (CPB15+). Bevacizumab was given at 15 mg/kg every three weeks. On this trial, 1215 patients received at least one dose of bevacizumab. The demographics of the safety population were similar to the demographics of the efficacy population.

Grades 3–4 adverse reactions occurring at a higher incidence (≥2%) in either of the bevacizumab arms versus the control arm were fatigue (CPB15+ - 9%, CPB15 - 6%, CPP - 6%), hypertension (CPB15+ - 10%, CPB15 - 6%, CPP - 2%), thrombocytopenia (CPB15+ - 21%, CPB15 - 20%, CPP - 15%) and leukopenia (CPB15+ - 51%, CPB15 - 53%, CPP - 50%). Adverse reactions are presented in Table 5.

Table 5: Grades 1–5 Adverse Reactions Occurring at Higher Incidence (≥5%) in Patients Receiving Bevacizumab with Chemotherapy vs. Chemotherapy Alone in Study GOG-0218
Adverse Reaction [NCI-CTC version 3,] | Bevacizumab with Carboplatin and Paclitaxel followed by Bevacizumab Alone [CPB15+,] (N=608) | Bevacizumab with Carboplatin and Paclitaxel [CPB15,] (N=607) | Carboplatin and Paclitaxel [CPP] (N=602)
General
Fatigue | 80% | 72% | 73%
Gastrointestinal
Nausea | 58% | 53% | 51%
Diarrhea | 38% | 40% | 34%
Stomatitis | 25% | 19% | 14%
Musculoskeletal and connective tissue
Arthralgia | 41% | 33% | 35%
Pain in extremity | 25% | 19% | 17%
Muscular weakness | 15% | 13% | 9%
Nervous system
Headache | 34% | 26% | 21%
Dysarthria | 12% | 10% | 2%
Vascular
Hypertension | 32% | 24% | 14%
Respiratory, thoracic and mediastinal
Epistaxis | 31% | 30% | 9%
Dyspnea | 26% | 28% | 20%
Nasal mucosal disorder | 10% | 7% | 4%

Platinum-Resistant Recurrent Epithelial Ovarian, Fallopian Tube, or Primary Peritoneal Cancer

The safety of bevacizumab was evaluated in 179 patients who received at least one dose of bevacizumab in a multicenter, open-label study (MO22224) in which patients were randomized (1:1) to bevacizumab with chemotherapy or chemotherapy alone in patients with platinum-resistant recurrent epithelial ovarian, fallopian tube, or primary peritoneal cancer that recurred within <6 months from the most recent platinum based therapy [see Clinical Studies (14.8)]. Patients were randomized to receive bevacizumab 10 mg/kg every 2 weeks or 15 mg/kg every 3 weeks. Patients had received no more than 2 prior chemotherapy regimens. The trial excluded patients with evidence of recto-sigmoid involvement by pelvic examination or bowel involvement on CT scan or clinical symptoms of bowel obstruction. Patients were treated until disease progression or unacceptable toxicity. Forty percent of patients on the chemotherapy alone arm received bevacizumab alone upon progression. The demographics of the safety population were similar to the demographics of the efficacy population.

Grades 3–4 adverse reactions occurring at a higher incidence (≥2%) in 179 patients receiving bevacizumab with chemotherapy compared to 181 patients receiving chemotherapy alone were hypertension (6.7% vs. 1.1%) and palmar-plantar erythrodysaesthesia syndrome (4.5% vs. 1.7%). Adverse reactions are presented in Table 6.

Table 6: Grades 2–4 Adverse Reactions Occurring at Higher Incidence (≥5%) in Patients Receiving Bevacizumab with Chemotherapy vs. Chemotherapy Alone in Study MO22224
Adverse Reaction [NCI-CTC version 3] | Bevacizumab with Chemotherapy (N=179) | Chemotherapy (N=181)
Hematology
Neutropenia | 31% | 25%
Vascular
Hypertension | 19% | 6%
Nervous system
Peripheral sensory neuropathy | 18% | 7%
General
Mucosal inflammation | 13% | 6%
Renal and urinary
Proteinuria | 12% | 0.6%
Skin and subcutaneous tissue
Palmar-plantar erythrodysaesthesia | 11% | 5%
Infections
Infection | 11% | 4%
Respiratory, thoracic and mediastinal
Epistaxis | 5% | 0%

Platinum-Sensitive Recurrent Epithelial Ovarian, Fallopian Tube, or Primary Peritoneal Cancer

Study AVF4095g

The safety of bevacizumab was evaluated in 247 patients who received at least one dose of bevacizumab in a double-blind study (AVF4095g) in patients with platinum-sensitive recurrent epithelial ovarian, fallopian tube, or primary peritoneal cancer [see Clinical Studies (14.9)]. Patients were randomized (1:1) to receive bevacizumab (15 mg/kg) or placebo every 3 weeks with carboplatin and gemcitabine for 6 to 10 cycles followed by bevacizumab or placebo alone until disease progression or unacceptable toxicity. The demographics of the safety population were similar to the demographics of the efficacy population.

Grades 3–4 adverse reactions occurring at a higher incidence (≥2%) in patients receiving bevacizumab with chemotherapy compared to placebo with chemotherapy were: thrombocytopenia (40% vs. 34%), nausea (4% vs. 1.3%), fatigue (6% vs. 4%), headache (4% vs. 0.9%), proteinuria (10% vs. 0.4%), dyspnea (4% vs. 1.7%), epistaxis (5% vs. 0.4%), and hypertension (17% vs. 0.9%). Adverse reactions are presented in Table 7.

Table 7: Grades 1–5 Adverse Reactions Occurring at Higher Incidence (≥5%) in Patients Receiving Bevacizumab with Chemotherapy vs. Placebo with Chemotherapy in Study AVF4095g
Adverse Reaction [NCI-CTC version 3] | Bevacizumab with Carboplatin and Gemcitabine (N=247) | Placebo with Carboplatin and Gemcitabine (N=233)
General
Fatigue | 82% | 75%
Mucosal inflammation | 15% | 10%
Gastrointestinal
Nausea | 72% | 66%
Diarrhea | 38% | 29%
Stomatitis | 15% | 7%
Hemorrhoids | 8% | 3%
Gingival bleeding | 7% | 0%
Hematology
Thrombocytopenia | 58% | 51%
Respiratory, thoracic and mediastinal
Epistaxis | 55% | 14%
Dyspnea | 30% | 24%
Cough | 26% | 18%
Oropharyngeal pain | 16% | 10%
Dysphonia | 13% | 3%
Rhinorrhea | 10% | 4%
Sinus congestion | 8% | 2%
Nervous system
Headache | 49% | 30%
Dizziness | 23% | 17%
Vascular
Hypertension | 42% | 9%
Musculoskeletal and connective tissue
Arthralgia | 28% | 19%
Back pain | 21% | 13%
Psychiatric
Insomnia | 21% | 15%
Renal and urinary
Proteinuria | 20% | 3%
Injury and procedural
Contusion | 17% | 9%
Infections
Sinusitis | 15% | 9%

Study GOG-0213

The safety of bevacizumab was evaluated in an open-label, controlled study (GOG-0213) in 325 patients with platinum-sensitive recurrent epithelial ovarian, fallopian tube, or primary peritoneal cancer, who have not received more than one previous regimen of chemotherapy [see Clinical Studies (14.9)]. Patients were randomized (1:1) to receive carboplatin and paclitaxel for 6 to 8 cycles or bevacizumab (15 mg/kg every 3 weeks) with carboplatin and paclitaxel for 6 to 8 cycles followed by bevacizumab as a single agent until disease progression or unacceptable toxicity. The demographics of the safety population were similar to the demographics of the efficacy population.

Grades 3–4 adverse reactions occurring at a higher incidence (≥2%) in patients receiving bevacizumab with chemotherapy compared to chemotherapy alone were: hypertension (11% vs. 0.6%), fatigue (8% vs. 3%), febrile neutropenia (6% vs. 3%), proteinuria (8% vs. 0%), abdominal pain (6% vs. 0.9%), hyponatremia (4% vs. 0.9%), headache (3% vs. 0.9%), and pain in extremity (3% vs. 0%). Adverse reactions are presented in Table 8.

Table 8: Grades 1–5 Adverse Reactions Occurring at Higher Incidence (≥5%) in Patients Receiving Bevacizumab with Chemotherapy vs. Chemotherapy Alone in Study GOG-0213
Adverse Reaction [NCI-CTC version 3] | Bevacizumab with Carboplatin and Paclitaxel (N=325) | Carboplatin and Paclitaxel (N=332)
Musculoskeletal and connective tissue
Arthralgia | 45% | 30%
Myalgia | 29% | 18%
Pain in extremity | 25% | 14%
Back pain | 17% | 10%
Muscular weakness | 13% | 8%
Neck pain | 9% | 0%
Vascular
Hypertension | 42% | 3%
Gastrointestinal
Diarrhea | 39% | 32%
Abdominal pain | 33% | 28%
Vomiting | 33% | 25%
Stomatitis | 33% | 16%
Nervous system
Headache | 38% | 20%
Dysarthria | 14% | 2%
Dizziness | 13% | 8%
Metabolism and nutrition
Decreased appetite | 35% | 25%
Hyperglycemia | 31% | 24%
Hypomagnesemia | 27% | 17%
Hyponatremia | 17% | 6%
Weight loss | 15% | 4%
Hypocalcemia | 12% | 5%
Hypoalbuminemia | 11% | 6%
Hyperkalemia | 9% | 3%
Respiratory, thoracic and mediastinal
Epistaxis | 33% | 2%
Dyspnea | 30% | 25%
Cough | 30% | 17%
Rhinitis allergic | 17% | 4%
Nasal mucosal disorder | 14% | 3%
Skin and subcutaneous tissue
Exfoliative rash | 23% | 16%
Nail disorder | 10% | 2%
Dry skin | 7% | 2%
Renal and urinary
Proteinuria | 17% | 1%
Increased blood creatinine | 13% | 5%
Hepatic
Increased aspartate aminotransferase | 15% | 9%
General
Chest pain | 8% | 2%
Infections
Sinusitis | 7% | 2%

6.2 Immunogenicity

As with all therapeutic proteins, there is a potential for immunogenicity. The detection of antibody formation is highly dependent on the sensitivity and the specificity of the assay. Additionally, the observed incidence of antibody (including neutralizing antibody) positivity in an assay may be influenced by several factors, including assay methodology, sample handling, timing of sample collection, concomitant medications, and underlying disease. For these reasons, comparison of the incidence of antibodies in the studies described below with the incidence of antibodies in other studies or to other bevacizumab products may be misleading.

In clinical studies for adjuvant treatment of a solid tumor, 0.6% (14/2233) of patients tested positive for treatment-emergent anti-bevacizumab antibodies as detected by an electrochemiluminescent (ECL) based assay. Among these 14 patients, three tested positive for neutralizing antibodies against bevacizumab using an enzyme-linked immunosorbent assay (ELISA). The clinical significance of these anti-bevacizumab antibodies is not known.

6.3 Postmarketing Experience

The following adverse reactions have been identified during postapproval use of bevacizumab products. Because these reactions are reported voluntarily from a population of uncertain size, it is not always possible to reliably estimate their frequency or establish a causal relationship to drug exposure.

General: Polyserositis

Cardiovascular: Pulmonary hypertension, Mesenteric venous occlusion

Gastrointestinal: Gastrointestinal ulcer, Intestinal necrosis, Anastomotic ulceration

Hemic and lymphatic: Pancytopenia

Hepatobiliary disorders: Gallbladder perforation

Musculoskeletal and Connective Tissue Disorders: Osteonecrosis of the jaw

Renal: Renal thrombotic microangiopathy (manifested as severe proteinuria)

Respiratory: Nasal septum perforation

Vascular: Arterial (including aortic) aneurysms, dissections, and rupture

7 DRUG INTERACTIONS

Effects of ZIRABEV on Other Drugs

No clinically meaningful effect on the pharmacokinetics of irinotecan or its active metabolite SN38, interferon alfa, carboplatin or paclitaxel was observed when bevacizumab was administered in combination with these drugs; however, 3 of the 8 patients receiving bevacizumab with paclitaxel and carboplatin had lower paclitaxel exposure after four cycles of treatment (at Day 63) than those at Day 0, while patients receiving paclitaxel and carboplatin alone had a greater paclitaxel exposure at Day 63 than at Day 0.

8 USE IN SPECIFIC POPULATIONS

8.1 Pregnancy

Risk Summary

Based on findings from animal studies and their mechanism of action [see Clinical Pharmacology (12.1)], bevacizumab products may cause fetal harm in pregnant women. Limited postmarketing reports describe cases of fetal malformations with use of bevacizumab products in pregnancy; however, these reports are insufficient to determine drug associated risks. In animal reproduction studies, intravenous administration of bevacizumab to pregnant rabbits every 3 days during organogenesis at doses approximately 1 to 10 times the clinical dose of 10 mg/kg produced fetal resorptions, decreased maternal and fetal weight gain and multiple congenital malformations including corneal opacities and abnormal ossification of the skull and skeleton including limb and phalangeal defects (see Data). Furthermore, animal models link angiogenesis and VEGF and VEGFR2 to critical aspects of female reproduction, embryo-fetal development, and postnatal development. Advise pregnant women of the potential risk to a fetus.

In the U.S. general population, the estimated background risk of major birth defects and miscarriage in clinically recognized pregnancies is 2% to 4% and 15% to 20%, respectively.

Data

Animal Data

Pregnant rabbits dosed with 10 mg/kg to 100 mg/kg bevacizumab (approximately 1 to 10 times the clinical dose of 10 mg/kg) every three days during the period of organogenesis (gestation day 6–18) exhibited decreases in maternal and fetal body weights and increased number of fetal resorptions. There were dose-related increases in the number of litters containing fetuses with any type of malformation (42% for the 0 mg/kg dose, 76% for the 30 mg/kg dose, and 95% for the 100 mg/kg dose) or fetal alterations (9% for the 0 mg/kg dose, 15% for the 30 mg/kg dose, and 61% for the 100 mg/kg dose). Skeletal deformities were observed at all dose levels, with some abnormalities including meningocele observed only at the 100 mg/kg dose level. Teratogenic effects included: reduced or irregular ossification in the skull, jaw, spine, ribs, tibia and bones of the paws; fontanel, rib and hindlimb deformities; corneal opacity; and absent hindlimb phalanges.

8.2 Lactation

Risk Summary

No data are available regarding the presence of bevacizumab products in human milk, the effects on the breast fed infant, or the effects on milk production. Human IgG is present in human milk, but published data suggest that breast milk antibodies do not enter the neonatal and infant circulation in substantial amounts. Because of the potential for serious adverse reactions in breastfed infants, advise women not to breastfeed during treatment with ZIRABEV and for 6 months after the last dose.

8.3 Females and Males of Reproductive Potential

Contraception

Females

Bevacizumab products may cause fetal harm when administered to a pregnant woman [see Use in Specific Populations (8.1)]. Advise females of reproductive potential to use effective contraception during treatment with ZIRABEV and for 6 months after the last dose.

Infertility

Females

Bevacizumab products increase the risk of ovarian failure and may impair fertility. Inform females of reproductive potential of the risk of ovarian failure prior to the first-dose of ZIRABEV. Long-term effects of bevacizumab products on fertility are not known.

In a clinical study of 179 premenopausal women randomized to receive chemotherapy with or without bevacizumab, the incidence of ovarian failure was higher in patients who received bevacizumab with chemotherapy (34%) compared to patients who received chemotherapy alone (2%). After discontinuing bevacizumab with chemotherapy, recovery of ovarian function occurred in 22% of these patients [see Warnings and Precautions (5.11), Adverse Reactions (6.1)].

8.4 Pediatric Use

The safety and effectiveness of bevacizumab products in pediatric patients have not been established. In published literature reports, cases of non-mandibular osteonecrosis have been observed in patients under the age of 18 years who received bevacizumab. Bevacizumab products are not approved for use in patients under the age of 18 years.

Antitumor activity was not observed among eight pediatric patients with relapsed GBM who received bevacizumab and irinotecan. Addition of bevacizumab to standard of care did not result in improved event-free survival in pediatric patients enrolled in two randomized clinical studies, one in high grade glioma (n=121) and one in metastatic rhabdomyosarcoma or non-rhabdomyosarcoma soft tissue sarcoma (n=154).

Based on the population pharmacokinetics analysis of data from 152 pediatric and young adult patients with cancer (7 months to 21 years of age), bevacizumab clearance normalized by body weight in pediatrics was comparable to that in adults.

Juvenile Animal Toxicity Data

Juvenile cynomolgus monkeys with open growth plates exhibited physeal dysplasia following 4 to 26 weeks exposure at 0.4 to 20 times the recommended human dose (based on mg/kg and exposure). The incidence and severity of physeal dysplasia were dose-related and were partially reversible upon cessation of treatment.

8.5 Geriatric Use

In an exploratory, pooled analysis of 1745 patients from five randomized, controlled studies, 35% of patients were ≥65 years old. The overall incidence of ATE was increased in all patients receiving bevacizumab with chemotherapy as compared to those receiving chemotherapy alone, regardless of age; however, the increase in the incidence of ATE was greater in patients ≥65 years (8% vs. 3%) as compared to patients <65 years (2% vs. 1%) [see Warnings and Precautions (5.4)].

11 DESCRIPTION

Bevacizumab-bvzr is a vascular endothelial growth factor inhibitor. Bevacizumab-bvzr is a recombinant humanized monoclonal IgG1 antibody that contains human framework regions and murine complementarity-determining regions. Bevacizumab-bvzr has an approximate molecular weight of 149 kDa. Bevacizumab-bvzr is produced in a mammalian cell (Chinese Hamster Ovary) expression system.

ZIRABEV (bevacizumab-bvzr) injection is a sterile, preservative-free, clear to slightly opalescent, colorless to pale brown solution in a single-dose vial for intravenous use. ZIRABEV contains bevacizumab-bvzr at a concentration of 25 mg/mL in either 100 mg/4 mL or 400 mg/16 mL single-dose vials.

Each mL of solution contains 25 mg bevacizumab-bvzr, edetate disodium dihydrate (0.05 mg), polysorbate 80 (0.2 mg), succinic acid (2.36 mg), sucrose (85 mg), and Water for Injection, USP. Sodium hydroxide is added to adjust the pH. The pH is 5.5.

12 CLINICAL PHARMACOLOGY

12.1 Mechanism of Action

Bevacizumab products bind VEGF and prevent the interaction of VEGF to its receptors (Flt-1 and KDR) on the surface of endothelial cells. The interaction of VEGF with its receptors leads to endothelial cell proliferation and new blood vessel formation in in vitro models of angiogenesis. Administration of bevacizumab to xenotransplant models of colon cancer in nude (athymic) mice caused reduction of microvascular growth and inhibition of metastatic disease progression.

12.3 Pharmacokinetics

The pharmacokinetic profile of bevacizumab was assessed using an assay that measures total serum bevacizumab concentrations (i.e., the assay did not distinguish between free bevacizumab and bevacizumab bound to VEGF ligand). Based on a population pharmacokinetic analysis of 491 patients who received 1 to 20 mg/kg of bevacizumab every week, every 2 weeks, or every 3 weeks, bevacizumab pharmacokinetics are linear and the predicted time to reach more than 90% of steady state concentration is 84 days. The accumulation ratio following a dose of 10 mg/kg of bevacizumab once every 2 weeks is 2.8.

Population simulations of bevacizumab exposures provide a median trough concentration of 80.3 mcg/mL on Day 84 (10th, 90th percentile: 45, 128) following a dose of 5 mg/kg once every two weeks.

Distribution

The mean (% coefficient of variation [CV%]) central volume of distribution is 2.9 (22%) L.

Elimination

The mean (CV%) clearance is 0.23 (33) L/day. The estimated half-life is 20 days (11 to 50 days).

Specific Populations

The clearance of bevacizumab varied by body weight, sex, and tumor burden. After correcting for body weight, males had a higher bevacizumab clearance (0.26 L/day vs. 0.21 L/day) and a larger central volume of distribution (3.2 L vs. 2.7 L) than females. Patients with higher tumor burden (at or above median value of tumor surface area) had a higher bevacizumab clearance (0.25 L/day vs. 0.20 L/day) than patients with tumor burdens below the median. In Study AVF2107g, there was no evidence of lesser efficacy (hazard ratio for overall survival) in males or patients with higher tumor burden treated with bevacizumab as compared to females and patients with low tumor burden.

13 NONCLINICAL TOXICOLOGY

13.1 Carcinogenesis, Mutagenesis, Impairment of Fertility

No studies have been conducted to assess potential of bevacizumab products for carcinogenicity or mutagenicity.

Bevacizumab products may impair fertility. Female cynomolgus monkeys treated with 0.4 to 20 times the recommended human dose of bevacizumab exhibited arrested follicular development or absent corpora lutea, as well as dose-related decreases in ovarian and uterine weights, endometrial proliferation, and the number of menstrual cycles. Following a 4- or 12-week recovery period, there was a trend suggestive of reversibility. After the 12-week recovery period, follicular maturation arrest was no longer observed, but ovarian weights were still moderately decreased. Reduced endometrial proliferation was no longer observed at the 12-week recovery time point; however, decreased uterine weight, absent corpora lutea, and reduced number of menstrual cycles remained evident.

13.2 Animal Toxicology and/or Pharmacology

Rabbits dosed with bevacizumab exhibited reduced wound healing capacity. Using full-thickness skin incision and partial thickness circular dermal wound models, bevacizumab dosing resulted in reductions in wound tensile strength, decreased granulation and re-epithelialization, and delayed time to wound closure.

14 CLINICAL STUDIES

14.1 Metastatic Colorectal Cancer

Study AVF2107g

The safety and efficacy of bevacizumab was evaluated in a double-blind, active-controlled study [AVF2107g (NCT00109070)] in 923 patients with previously untreated mCRC who were randomized (1:1:1) to placebo with bolus-IFL (irinotecan 125 mg/m^2, fluorouracil 500 mg/m^2, and leucovorin 20 mg/m^2 given once weekly for 4 weeks every 6 weeks), bevacizumab (5 mg/kg every 2 weeks) with bolus-IFL, or bevacizumab (5 mg/kg every 2 weeks) with fluorouracil and leucovorin. Enrollment to the bevacizumab with fluorouracil and leucovorin arm was discontinued, after enrollment of 110 patients in accordance with the protocol-specified adaptive design. Bevacizumab was continued until disease progression or unacceptable toxicity or for a maximum of 96 weeks. The main outcome measure was overall survival (OS).

The median age was 60 years; 60% were male, 79% were White, 57% had an ECOG performance status of 0, 21% had a rectal primary and 28% received prior adjuvant chemotherapy. The dominant site of disease was extra-abdominal in 56% of patients and was the liver in 38% of patients.

The addition of bevacizumab improved survival across subgroups defined by age (<65 years, ≥65 years) and sex. Results are presented in Table 9 and Figure 1.

Table 9: Efficacy Results in Study AVF2107g
Efficacy Parameter | Bevacizumab with bolus-IFL (N=402) | Placebo with bolus-IFL (N=411)
Overall Survival
Median, in months | 20.3 | 15.6
Hazard ratio (95% CI) | 0.66 (0.54, 0.81)
p-value [by stratified log-rank test.] | < 0.001
Progression-Free Survival
Median, in months | 10.6 | 6.2
Hazard ratio (95% CI) | 0.54 (0.45, 0.66)
p-value | < 0.001
Overall Response Rate
Rate (%) | 45% | 35%
p-value [by χ^2 test.] | < 0.01
Duration of Response
Median, in months | 10.4 | 7.1

Figure 1: Kaplan-Meier Curves for Duration of Survival in Metastatic Colorectal Cancer in Study AVF2107g

Among the 110 patients randomized to bevacizumab with fluorouracil and leucovorin, median OS was 18.3 months, median progression-free survival (PFS) was 8.8 months, overall response rate (ORR) was 39%, and median duration of response was 8.5 months.

Study E3200

The safety and efficacy of bevacizumab were evaluated in a randomized, open-label, active-controlled study [E3200 (NCT00025337)] in 829 patients who were previously treated with irinotecan and fluorouracil for initial therapy for metastatic disease or as adjuvant therapy. Patients were randomized (1:1:1) to FOLFOX4 (Day 1: oxaliplatin 85 mg/m^2 and leucovorin 200 mg/m^2 concurrently, then fluorouracil 400 mg/m^2 bolus followed by 600 mg/m^2 continuously; Day 2: leucovorin 200 mg/m^2, then fluorouracil 400 mg/m^2 bolus followed by 600 mg/m^2 continuously; every 2 weeks), bevacizumab (10 mg/kg every 2 weeks prior to FOLFOX4 on Day 1) with FOLFOX4, or bevacizumab alone (10 mg/kg every 2 weeks). Bevacizumab was continued until disease progression or unacceptable toxicity. The main outcome measure was OS.

The bevacizumab alone arm was closed to accrual after enrollment of 244 of the planned 290 patients following a planned interim analysis by the data monitoring committee based on evidence of decreased survival compared to FOLFOX4 alone.

The median age was 61 years; 60% were male, 87% were White, 49% had an ECOG performance status of 0, 26% received prior radiation therapy, and 80% received prior adjuvant chemotherapy, 99% received prior irinotecan with or without fluorouracil for metastatic disease, and 1% received prior irinotecan and fluorouracil as adjuvant therapy.

The addition of bevacizumab to FOLFOX4 resulted in significantly longer survival as compared to FOLFOX4 alone; median OS was 13.0 months vs. 10.8 months [hazard ratio (HR) 0.75 (95% CI: 0.63, 0.89), p-value of 0.001 stratified log-rank test] with clinical benefit seen in subgroups defined by age (<65 years, ≥65 years) and sex. PFS and ORR based on investigator assessment were higher in patients receiving bevacizumab with FOLFOX4.

Study TRC-0301

The activity of bevacizumab with fluorouracil (as bolus or infusion) and leucovorin was evaluated in a single arm study [TRC-0301 (NCT00066846)] enrolling 339 patients with mCRC with disease progression following both irinotecan- and oxaliplatin-based chemotherapy. Seventy-three percent of patients received concurrent bolus fluorouracil and leucovorin. One objective partial response was verified in the first 100 evaluable patients for an ORR of 1% (95% CI: 0%, 5.5%).

Study ML18147

The safety and efficacy of bevacizumab were evaluated in a prospective, randomized, open-label, multinational, controlled study [ML18147 (NCT00700102)] in 820 patients with histologically confirmed mCRC who had progressed on a first-line bevacizumab-containing regimen. Patients were excluded if they progressed within 3 months of initiating first-line chemotherapy and if they received bevacizumab for less than 3 consecutive months in the first-line setting. Patients were randomized (1:1) within 3 months after discontinuing bevacizumab as first-line treatment to receive fluoropyrimidine-irinotecan- or fluoropyrimidine-oxaliplatin-based chemotherapy with or without bevacizumab (5 mg/kg every 2 weeks or 7.5 mg/kg every 3 weeks). The choice of second-line treatment was contingent upon first-line chemotherapy. Second-line treatment was administered until progressive disease or unacceptable toxicity. The main outcome measure was OS. A secondary outcome measure was ORR.

The median age was 63 years (21 to 84 years); 64% were male, 52% had an ECOG performance status of 1, 44% had an ECOG performance status of 0, 58% received irinotecan-based therapy as first-line treatment, 55% progressed on first-line treatment within 9 months, and 77% received their last dose of bevacizumab as first-line treatment within 42 days of being randomized. Second-line chemotherapy regimens were generally balanced between each arm.

The addition of bevacizumab to fluoropyrimidine-based chemotherapy resulted in a statistically significant prolongation of OS and PFS. There was no significant difference in ORR. Results are presented in Table 10 and Figure 2.

Table 10: Efficacy Results in Study ML18147
Efficacy Parameter | Bevacizumab with Chemotherapy (N=409) | Chemotherapy (N=411)
Overall Survival [p = 0.0057 by unstratified log-rank test.]
Median, in months | 11.2 | 9.8
Hazard ratio (95% CI) | 0.81 (0.69, 0.94)
Progression-Free Survival [p-value < 0.0001 by unstratified log-rank test.]
Median, in months | 5.7 | 4.0
Hazard ratio (95% CI) | 0.68 (0.59, 0.78)

Figure 2: Kaplan-Meier Curves for Duration of Survival in Metastatic Colorectal Cancer in Study ML18147

14.2 Lack of Efficacy in Adjuvant Treatment of Colon Cancer

Lack of efficacy of bevacizumab as an adjunct to standard chemotherapy for the adjuvant treatment of colon cancer was determined in two randomized, open-label, multicenter clinical studies.

The first study [BO17920 (NCT00112918)] was conducted in 3451 patients with high-risk stage II and III colon cancer, who had undergone surgery for colon cancer with curative intent. Patients were randomized to receive bevacizumab at a dose equivalent to 2.5 mg/kg/week on either a 2-weekly schedule with FOLFOX4 (N=1155) or on a 3-weekly schedule with XELOX (N=1145) or FOLFOX4 alone (N=1151). The main outcome measure was disease free survival (DFS) in patients with stage III colon cancer.

The median age was 58 years; 54% were male, 84% were White and 29% were ≥65 years. Eighty-three percent had stage III disease.

The addition of bevacizumab to chemotherapy did not improve DFS. As compared to FOLFOX4 alone, the proportion of stage III patients with disease recurrence or with death due to disease progression were numerically higher for patients receiving bevacizumab with FOLFOX4 or with XELOX. The hazard ratios for DFS were 1.17 (95% CI: 0.98, 1.39) for bevacizumab with FOLFOX4 versus FOLFOX4 alone and 1.07 (95% CI: 0.90, 1.28) for bevacizumab with XELOX versus FOLFOX4 alone. The hazard ratios for OS were 1.31 (95% CI: 1.03, 1.67) and 1.27 (95% CI: 1, 1.62) for the comparison of bevacizumab with FOLFOX4 versus FOLFOX4 alone and bevacizumab with XELOX versus FOLFOX4 alone, respectively. Similar lack of efficacy for DFS was observed in the bevacizumab-containing arms compared to FOLFOX4 alone in the high-risk stage II cohort.

In a second study [NSABP-C-08 (NCT00096278)], patients with stage II and III colon cancer who had undergone surgery with curative intent, were randomized to receive either bevacizumab administered at a dose equivalent to 2.5 mg/kg/week with mFOLFOX6 (N=1354) or mFOLFOX6 alone (N=1356). The median age was 57 years, 50% were male and 87% White. Seventy-five percent had stage III disease. The main outcome was DFS among stage III patients. The HR for DFS was 0.92 (95% CI: 0.77, 1.10). OS was not significantly improved with the addition of bevacizumab to mFOLFOX6 [HR 0.96 (95% CI: 0.75, 1.22)].

14.3 First-Line Non–Squamous Non–Small Cell Lung Cancer

Study E4599

The safety and efficacy of bevacizumab as first-line treatment of patients with locally advanced, metastatic, or recurrent non-squamous NSCLC was studied in a single, large, randomized, active-controlled, open-label, multicenter study [E4599 (NCT00021060)]. A total of 878 chemotherapy-naïve patients with locally advanced, metastatic or recurrent non–squamous NSCLC were randomized (1:1) to receive six 21-day cycles of paclitaxel (200 mg/m^2) and carboplatin (AUC 6) with or without bevacizumab 15 mg/kg. After completing or discontinuing chemotherapy, patients randomized to receive bevacizumab continued to receive bevacizumab alone until disease progression or until unacceptable toxicity. The trial excluded patients with predominant squamous histology (mixed cell type tumors only), CNS metastasis, gross hemoptysis (1/2 teaspoon or more of red blood), unstable angina, or receiving therapeutic anticoagulation. The main outcome measure was duration of survival.

The median age was 63 years; 54% were male, 43% were ≥65 years, and 28% had ≥5% weight loss at study entry. Eleven percent had recurrent disease. Of the 89% with newly diagnosed NSCLC, 12% had Stage IIIB with malignant pleural effusion and 76% had Stage IV disease.

OS was statistically significantly longer for patients receiving bevacizumab with paclitaxel and carboplatin compared with those receiving chemotherapy alone. Median OS was 12.3 months vs. 10.3 months [HR 0.80 (95% CI: 0.68, 0.94), final p-value of 0.013, stratified log-rank test]. Based on investigator assessment which was not independently verified, patients were reported to have longer PFS with bevacizumab with paclitaxel and carboplatin compared to chemotherapy alone. Results are presented in Figure 3.

Figure 3: Kaplan-Meier Curves for Duration of Survival in First-Line Non-Squamous Non-Small Cell Lung Cancer in Study E4599

In an exploratory analysis across patient subgroups, the impact of bevacizumab on OS was less robust in the following subgroups: women [HR 0.99 (95% CI: 0.79, 1.25)], patients ≥65 years [HR 0.91 (95% CI: 0.72, 1.14)] and patients with ≥5% weight loss at study entry [HR 0.96 (95% CI: 0.73, 1.26)].

Study BO17704

The safety and efficacy of bevacizumab in patients with locally advanced, metastatic or recurrent non-squamous NSCLC, who had not received prior chemotherapy was studied in another randomized, double-blind, placebo-controlled study [BO17704 (NCT00806923)]. A total of 1043 patients were randomized (1:1:1) to receive cisplatin and gemcitabine with placebo, bevacizumab 7.5 mg/kg or bevacizumab 15 mg/kg. The main outcome measure was PFS. Secondary outcome measure was OS.

The median age was 58 years; 36% were female and 29% were ≥65 years. Eight percent had recurrent disease and 77% had Stage IV disease.

PFS was significantly higher in both bevacizumab-containing arms compared to the placebo arm [HR 0.75 (95% CI: 0.62, 0.91), p-value of 0.0026 for bevacizumab 7.5 mg/kg and HR 0.82 (95% CI: 0.68, 0.98), p-value of 0.0301 for bevacizumab 15 mg/kg]. The addition of bevacizumab to cisplatin and gemcitabine failed to demonstrate an improvement in the duration of OS [HR 0.93 (95% CI: 0.78, 1.11), p-value of 0.420 for bevacizumab 7.5 mg/kg and HR 1.03 (95% CI: 0.86, 1.23), p-value of 0.761 for bevacizumab 15 mg/kg].

14.4 Recurrent Glioblastoma

Study EORTC 26101

The safety and efficacy of bevacizumab were evaluated in a multicenter, randomized (2:1), open-label study in patients with recurrent GBM (EORTC 26101, NCT01290939). Patients with first progression following radiotherapy and temozolomide were randomized (2:1) to receive bevacizumab (10 mg/kg every 2 weeks) with lomustine (90 mg/m^2 every 6 weeks) or lomustine (110 mg/m^2 every 6 weeks) alone until disease progression or unacceptable toxicity. Randomization was stratified by World Health Organization performance status (0 vs. >0), steroid use (yes vs. no), largest tumor diameter (≤40 vs. >40 mm), and institution. The main outcome measure was OS. Secondary outcome measures were investigator-assessed PFS and ORR per the modified Response Assessment in Neuro-oncology (RANO) criteria, health related quality of life (HRQoL), cognitive function, and corticosteroid use.

A total of 432 patients were randomized to receive lomustine alone (N=149) or bevacizumab with lomustine (N=283). The median age was 57 years; 24.8% of patients were ≥65 years. The majority of patients with were male (61%); 66% had a WHO performance status score >0; and in 56% the largest tumor diameter was ≤40 mm. Approximately 33% of patients randomized to receive lomustine received bevacizumab following documented progression.

No difference in OS (HR 0.91, p-value of 0.4578) was observed between arms; therefore, all secondary outcome measures are descriptive only. PFS was longer in the bevacizumab with lomustine arm [HR 0.52 (95% CI: 0.41, 0.64)] with a median PFS of 4.2 months in the bevacizumab with lomustine arm and 1.5 months in the lomustine arm. Among the 50% of patients receiving corticosteroids at the time of randomization, a higher percentage of patients in the bevacizumab with lomustine arm discontinued corticosteroids (23% vs. 12%).

Study AVF3708g and Study NCI 06-C-0064E

The efficacy and safety of bevacizumab 10 mg/kg every 2 weeks in patients with previously treated GBM were evaluated in one single arm single center study (NCI 06-C-0064E) and a randomized noncomparative multicenter study [AVF3708g(NCT00345163)]. Response rates in both studies were evaluated based on modified WHO criteria that considered corticosteroid use. In AVF3708g, the response rate was 25.9% (95% CI: 17%, 36.1%) with a median duration of response of 4.2 months (95% CI: 3, 5.7). In Study NCI 06-C-0064E, the response rate was 19.6% (95% CI: 10.9%, 31.3%) with a median duration of response of 3.9 months (95% CI: 2.4, 17.4).

14.5 Metastatic Renal Cell Carcinoma

Study BO17705

The safety and efficacy of bevacizumab were evaluated in patients with treatment-naïve mRCC in a multicenter, randomized, double-blind, international study [BO17705 (NCT00738530)] comparing interferon alfa and bevacizumab versus interferon alfa and placebo. A total of 649 patients who had undergone a nephrectomy were randomized (1:1) to receive either bevacizumab (10 mg/kg every 2 weeks; N=327) or placebo (every 2 weeks; N=322) with interferon alfa (9 MIU subcutaneously three times weekly for a maximum of 52 weeks). Patients were treated until disease progression or unacceptable toxicity. The main outcome measure was investigator-assessed PFS. Secondary outcome measures were ORR and OS.

The median age was 60 years (18 to 82 years); 70% were male and 96% were White. The study population was characterized by Motzer scores as follows: 28% favorable (0), 56% intermediate (1–2), 8% poor (3–5), and 7% missing.

PFS was statistically significantly prolonged among patients receiving bevacizumab compared to placebo; median PFS was 10.2 months vs. 5.4 months [HR 0.60 (95% CI: 0.49, 0.72), p-value < 0.0001, stratified log-rank test]. Among the 595 patients with measurable disease, ORR was also significantly higher (30% vs. 12%, p-value < 0.0001, stratified CMH test). There was no improvement in OS based on the final analysis conducted after 444 deaths, with a median OS of 23 months in the patients receiving bevacizumab with interferon alfa and 21 months in patients receiving interferon alone [HR 0.86, (95% CI: 0.72, 1.04)]. Results are presented in Figure 4.

Figure 4: Kaplan-Meier Curves for Progression-Free Survival in Metastatic Renal Cell Carcinoma in Study BO17705

14.6 Persistent, Recurrent, or Metastatic Cervical Cancer

Study GOG-0240

The safety and efficacy of bevacizumab were evaluated in patients with persistent, recurrent, or metastatic cervical cancer in a randomized, four-arm, multicenter study comparing bevacizumab with chemotherapy versus chemotherapy alone [GOG-0240 (NCT00803062)]. A total of 452 patients were randomized (1:1:1:1) to receive paclitaxel and cisplatin with or without bevacizumab, or paclitaxel and topotecan with or without bevacizumab.

The dosing regimens for bevacizumab, paclitaxel, cisplatin and topotecan were as follows:

- Day 1: Paclitaxel 135 mg/m^2 over 24 hours, Day 2: cisplatin 50 mg/m^2 with bevacizumab;
- Day 1: Paclitaxel 175 mg/m^2 over 3 hours, Day 2: cisplatin 50 mg/m^2 with bevacizumab;
- Day 1: Paclitaxel 175 mg/m^2 over 3 hours with cisplatin 50 mg/m^2 with bevacizumab;
- Day 1: Paclitaxel 175 mg/m^2 over 3 hours with bevacizumab, Days 1–3: topotecan IV 0.75 mg/m^2 over 30 minutes.

Patients were treated until disease progression or unacceptable adverse reactions. The main outcome measure was OS. Secondary outcome measures included ORR.

The median age was 48 years (20 to 85 years). Of the 452 patients randomized at baseline, 78% of patients were White, 80% had received prior radiation, 74% had received prior chemotherapy concurrent with radiation, and 32% had a platinum-free interval (PFI) of less than 6 months. Patients had a GOG performance status of 0 (58%) or 1 (42%). Demographic and disease characteristics were balanced across arms.

Results are presented in Figure 5 and Table 11.

Figure 5: Kaplan-Meier Curves for Overall Survival in Persistent, Recurrent, or Metastatic Cervical Cancer in Study GOG-0240

Table 11: Efficacy Results in Study GOG-0240
Efficacy Parameter | Bevacizumab with Chemotherapy (N=227) | Chemotherapy (N=225)
Overall Survival
Median, in months [Kaplan-Meier estimates.] | 16.8 | 12.9
Hazard ratio (95% CI) | 0.74 (0.58; 0.94)
p-value [log-rank test (stratified).] | 0.0132

The ORR was higher in patients who received bevacizumab with chemotherapy [45% (95% CI: 39, 52)] compared to patients who received chemotherapy alone [34% (95% CI: 28, 40)].

Table 12: Efficacy Results in Study GOG-0240
Efficacy Parameter | Topotecan and Paclitaxel with or without Bevacizumab (N=223) | Cisplatin and Paclitaxel with or without Bevacizumab (N=229)
Overall Survival
Median, in months [Kaplan-Meier estimates.] | 13.3 | 15.5
Hazard ratio (95% CI) | 1.15 (0.91, 1.46)
p-value | 0.23

The HR for OS with bevacizumab with cisplatin and paclitaxel as compared to cisplatin and paclitaxel alone was 0.72 (95% CI: 0.51, 1.02). The HR for OS with bevacizumab with topotecan and paclitaxel as compared to topotecan and paclitaxel alone was 0.76 (95% CI: 0.55, 1.06).

14.7 Stage III or IV Epithelial Ovarian, Fallopian Tube, or Primary Peritoneal Cancer Following Initial Surgical Resection

Study GOG-0218

The safety and efficacy of bevacizumab were evaluated in a multicenter, randomized, double-blind, placebo-controlled, three arm study [Study GOG-0218 (NCT00262847)] evaluating the effect of adding bevacizumab to carboplatin and paclitaxel for the treatment of patients with stage III or IV epithelial ovarian, fallopian tube, or primary peritoneal cancer (N=1873) following initial surgical resection. Patients were randomized (1:1:1) to one of the following arms:

- CPP: carboplatin (AUC 6) and paclitaxel (175 mg/m^2) for six cycles, with concurrent placebo started at cycle 2, followed by placebo alone every three weeks for a total of up to 22 cycles of therapy (n=625) or
- CPB15: carboplatin (AUC 6) and paclitaxel (175 mg/m^2) for six cycles, with concurrent bevacizumab started at cycle 2, followed by placebo alone every three weeks for a total of up to 22 cycles of therapy (n=625) or
- CPB15+: carboplatin (AUC 6) and paclitaxel (175 mg/m^2) for six cycles, with concurrent bevacizumab started at cycle 2, followed by bevacizumab as a single agent every three weeks for a total of up to 22 cycles of therapy (n=623).

The main outcome measure was investigator-assessed PFS. OS was a secondary outcome measure.

The median age was 60 years (range 22–89 years) and 28% of patients were >65 years of age. Overall, approximately 50% of patients had a GOG PS of 0 at baseline, and 43% a GOG PS score of 1. Patients had either epithelial ovarian cancer (83%), primary peritoneal cancer (15%), or fallopian tube cancer (2%). Serous adenocarcinoma was the most common histologic type (85% in CPP and CPB15 arms, 86% in CPB15+ arm). Overall, approximately 34% of patients had resected FIGO Stage III with residual disease <1 cm, 40% had resected Stage III with residual disease >1 cm, and 26% had resected Stage IV disease.

The majority of patients in all three treatment arms received subsequent antineoplastic treatment, 78.1% in the CPP arm, 78.6% in the CPB15 arm, and 73.2% in the CPB15+ arm. A higher proportion of patients in the CPP arm (25.3%) and CPB15 arm (26.6%) received at least one anti-angiogenic (including bevacizumab) treatment after discontinuing from study compared with the CPB15+ arm (15.6%).

Study results are presented in Table 13 and Figure 6.

Table 13: Efficacy Results in Study GOG-0218
Efficacy Parameter | Bevacizumab with Carboplatin and Paclitaxel followed by Bevacizumab Alone (N=623) | Bevacizumab with Carboplatin and Paclitaxel (N=625) | Carboplatin and Paclitaxel (N=625)
Progression-Free Survival per Investigator
Median, in months | 18.2 | 12.8 | 12.0
Hazard ratio (95% CI) [Relative to the control arm; stratified hazard ratio.] | 0.62 (0.52, 0.75) | 0.83 (0.70, 0.98)
p-value [Two-sided p-value based on re-randomization test.] | < 0.0001 | NS
Overall Survival [Final overall survival analysis.]
Median, in months | 43.8 | 38.8 | 40.6
Hazard ratio (95% CI) | 0.89 (0.76, 1.05) | 1.06 (0.90, 1.24)
NS=not significant.

Figure 6: Kaplan-Meier Curves for Investigator-Assessed Progression-Free Survival in Stage III or IV Epithelial Ovarian, Fallopian Tube, or Primary Peritoneal Cancer Following Initial Surgical Resection in Study GOG-0218

14.8 Platinum-Resistant Recurrent Epithelial Ovarian, Fallopian Tube, or Primary Peritoneal Cancer

Study MO22224

The safety and efficacy of bevacizumab were evaluated in a multicenter, open-label, randomized study [MO22224 (NCT00976911)] comparing bevacizumab with chemotherapy versus chemotherapy alone in patients with platinum-resistant recurrent epithelial ovarian, fallopian tube, or primary peritoneal cancer that recurred within <6 months from the most recent platinum-based therapy (N=361). Patients had received no more than 2 prior chemotherapy regimens. Patients received one of the following chemotherapy regimens at the discretion of the investigator: paclitaxel (80 mg/m^2 on days 1, 8, 15 and 22 every 4 weeks); pegylated liposomal doxorubicin (40 mg/m^2 on day 1 every 4 weeks); or topotecan (4 mg/m^2 on days 1, 8 and 15 every 4 weeks or 1.25 mg/m^2 on days 1–5 every 3 weeks). Patients were treated until disease progression, unacceptable toxicity, or withdrawal. Forty percent of patients on the chemotherapy alone arm received bevacizumab alone upon progression. The main outcome measure was investigator-assessed PFS. Secondary outcome measures were ORR and OS.

The median age was 61 years (25 to 84 years) and 37% of patients were ≥65 years. Seventy-nine percent had measurable disease at baseline, 87% had baseline CA-125 levels ≥2 times ULN and 31% had ascites at baseline. Seventy-three percent had a PFI of 3 months to 6 months and 27% had PFI of <3 months. ECOG performance status was 0 for 59%, 1 for 34%, and 2 for 7% of the patients.

The addition of bevacizumab to chemotherapy demonstrated a statistically significant improvement in investigator-assessed PFS, which was supported by a retrospective independent review analysis. Results for the ITT population are presented in Table 14 and Figure 7. Results for the separate chemotherapy cohorts are presented in Table 15.

Table 14: Efficacy Results in Study MO22224
Efficacy Parameter | Bevacizumab with Chemotherapy (N=179) | Chemotherapy (N=182)
Progression-Free Survival per Investigator
Median (95% CI), in months | 6.8 (5.6, 7.8) | 3.4 (2.1, 3.8)
Hazard ratio (95% CI) [per stratified Cox proportional hazards model.] | 0.38 (0.30, 0.49)
p-value [per stratified log-rank test.] | < 0.0001
Overall Survival
Median (95% CI), in months | 16.6 (13.7, 19.0) | 13.3 (11.9, 16.4)
Hazard ratio (95% CI) | 0.89 (0.69, 1.14)
Overall Response Rate
Number of patients with measurable disease at baseline | 142 | 144
Rate, % (95% CI) | 28% (21%, 36%) | 13% (7%, 18%)
Duration of Response
Median, in months | 9.4 | 5.4

Figure 7: Kaplan-Meier Curves for Investigator-Assessed Progression-Free Survival in Platinum-Resistant Recurrent Epithelial Ovarian, Fallopian Tube, or Primary Peritoneal Cancer in Study MO22224

Table 15: Efficacy Results in Study MO22224 by Chemotherapy
Efficacy Parameter | Paclitaxel |  | Topotecan |  | Pegylated Liposomal Doxorubicin
Efficacy Parameter | Bevacizumab with Chemotherapy | Chemotherapy | Bevacizumab with Chemotherapy | Chemotherapy | Bevacizumab with Chemotherapy | Chemotherapy
Efficacy Parameter | (N=60) | (N=55) | (N=57) | (N=63) | (N=62) | (N=64)
Progression-Free Survival per Investigator
Median, in months (95% CI) | 9.6 (7.8, 11.5) | 3.9 (3.5, 5.5) | 6.2 (5.3, 7.6) | 2.1 (1.9, 2.3) | 5.1 (3.9, 6.3) | 3.5 (1.9, 3.9)
Hazard ratio [per stratified Cox proportional hazards model.] (95% CI) | 0.47 (0.31, 0.72) |  | 0.24 (0.15, 0.38) |  | 0.47 (0.32, 0.71)
Overall Survival
Median, in months (95% CI) | 22.4 (16.7, 26.7) | 13.2 (8.2, 19.7) | 13.8 (11.0, 18.3) | 13.3 (10.4, 18.3) | 13.7 (11.0, 18.3) | 14.1 (9.9, 17.8)
Hazard ratio (95% CI) | 0.64 (0.41, 1.01) |  | 1.12 (0.73, 1.73) |  | 0.94 (0.63, 1.42)
Overall Response Rate
Number of patients with measurable disease at baseline | 45 | 43 | 46 | 50 | 51 | 51
Rate, % (95% CI) | 53 (39, 68) | 30 (17, 44) | 17 (6, 28) | 2 (0, 6) | 16 (6, 26) | 8 (0, 15)
Duration of Response
Median, in months | 11.6 | 6.8 | 5.2 | NE | 8.0 | 4.6
NE=Not Estimable.

14.9 Platinum-Sensitive Recurrent Epithelial Ovarian, Fallopian Tube, or Primary Peritoneal Cancer

Study AVF4095g

The safety and efficacy of bevacizumab were evaluated in a randomized, double-blind, placebo-controlled study [AVF4095g (NCT00434642)] studying bevacizumab with chemotherapy versus chemotherapy alone in the treatment of patients with platinum-sensitive recurrent epithelial ovarian, fallopian tube, or primary peritoneal cancer who have not received prior chemotherapy in the recurrent setting or prior bevacizumab treatment (N=484). Patients were randomized (1:1) to receive bevacizumab (15 mg/kg day 1) or placebo every 3 weeks with carboplatin (AUC 4, day 1) and gemcitabine (1000 mg/m^2 on days 1 and 8) for 6 to 10 cycles followed by bevacizumab or placebo alone until disease progression or unacceptable toxicity. The main outcome measures were investigator-assessed PFS. Secondary outcome measures were ORR and OS.

The median age was 61 years (28 to 87 years) and 37% of patients were ≥65 years. All patients had measurable disease at baseline, 74% had baseline CA-125 levels >ULN (35 U/mL). The PFI was 6 months to 12 months in 42% of patients and >12 months in 58% of patients. The ECOG performance status was 0 or 1 for 99.8% of patients.

A statistically significant prolongation in PFS was demonstrated among patients receiving bevacizumab with chemotherapy compared to those receiving placebo with chemotherapy (Table 16 and Figure 8). Independent radiology review of PFS was consistent with investigator assessment [HR 0.45 (95% CI: 0.35, 0.58)]. OS was not significantly improved with the addition of bevacizumab to chemotherapy [HR 0.95 (95% CI: 0.77, 1.17)].

Table 16: Efficacy Results in Study AVF4095g
Efficacy Parameter | Bevacizumab with Gemcitabine and Carboplatin (N=242) | Placebo with Gemcitabine and Carboplatin (N=242)
Progression-Free Survival
Median, in months | 12.4 | 8.4
Hazard ratio (95% CI) | 0.46 (0.37, 0.58)
p-value | < 0.0001
Overall Response Rate
% patients with overall response | 78% | 57%
p-value | < 0.0001

Figure 8: Kaplan-Meier Curves for Progression-Free Survival in Platinum-Sensitive Recurrent Epithelial Ovarian, Fallopian Tube, or Primary Peritoneal Cancer in Study AVF4095g

Study GOG-0213

The safety and efficacy of bevacizumab were evaluated in a randomized, controlled, open-label study [Study GOG-0213 (NCT00565851)] of bevacizumab with chemotherapy versus chemotherapy alone in the treatment of patients with platinum-sensitive recurrent epithelial ovarian, fallopian tube, or primary peritoneal cancer, who have not received more than one previous regimen of chemotherapy (N=673). Patients were randomized (1:1) to receive carboplatin (AUC 5) and paclitaxel (175 mg/m^2 IV over 3 hours) every 3 weeks for 6 to 8 cycles (N=336) or bevacizumab (15 mg/kg) every 3 weeks with carboplatin (AUC 5) and paclitaxel (175 mg/m^2 IV over 3 hours) for 6 to 8 cycles followed by bevacizumab (15 mg/kg every 3 weeks) as a single agent until disease progression or unacceptable toxicity. The main outcome measure was OS. Other outcome measures were investigator-assessed PFS, and ORR.

The median age was 60 years (23 to 85 years) and 33% of patients were ≥65 years. Eighty-three percent had measurable disease at baseline and 74% had abnormal CA-125 levels at baseline. Ten percent of patients had received prior bevacizumab. Twenty-six percent had a PFI of 6 months to 12 months and 74% had a PFI of >12 months. GOG performance status was 0 or 1 for 99% of patients.

Results are presented in Table 17 and Figure 9.

Table 17: Efficacy Results in Study GOG-0213
Efficacy Parameter | Bevacizumab with Carboplatin and Paclitaxel (N=337) | Carboplatin and Paclitaxel (N=336)
Overall Survival
Median, in months | 42.6 | 37.3
Hazard ratio (95% CI) (IVRS) [HR was estimated from Cox proportional hazards models stratified by the duration of treatment free-interval prior to enrolling onto this study per IVRS (interactive voice response system) and secondary surgical debulking status.] | 0.84 (0.69, 1.01)
Hazard ratio (95% CI) (eCRF) [HR was estimated from Cox proportional hazards models stratified by the duration of PFI prior to enrolling onto this study per eCRF (electronic case report form) and secondary surgical debulking status.] | 0.82 (0.68, 0.996)
Progression-Free Survival
Median, in months | 13.8 | 10.4
Hazard ratio (95% CI) (IVRS) | 0.61 (0.51, 0.72)
Overall Response Rate
Number of patients with measurable disease at baseline | 274 | 286
Rate, % | 213 (78%) | 159 (56%)

Figure 9: Kaplan-Meier Curves for Overall Survival in Platinum-Sensitive Recurrent Epithelial Ovarian, Fallopian Tube, or Primary Peritoneal Cancer in Study GOG-0213

16 HOW SUPPLIED/STORAGE AND HANDLING

ZIRABEV (bevacizumab-bvzr) injection is a clear to slightly opalescent, colorless to pale brown, sterile solution for intravenous infusion supplied in a carton containing one single-dose vial in the following strengths:

- 100 mg/4 mL (25 mg/mL) (NDC 0069-0315-01)
- 400 mg/16 mL (25 mg/mL) (NDC 0069-0342-01)

STORAGE AND HANDLING

Store refrigerated at 2°C to 8°C (36°F to 46°F) in the original carton until time of use to protect from light. Do not freeze or shake the vial or carton.

17 PATIENT COUNSELING INFORMATION

Gastrointestinal Perforations and Fistulae

Bevacizumab products may increase the risk of developing gastrointestinal perforations and fistulae. Advise patients to immediately contact their healthcare provider for high fever, rigors, persistent or severe abdominal pain, severe constipation, or vomiting [see Warnings and Precautions (5.1)].

Surgery and Wound Healing Complications

Bevacizumab products can increase the risk of wound healing complications. Instruct patients not to undergo surgery without first discussing this potential risk with their healthcare provider [see Warnings and Precautions (5.2)].

Hemorrhage

Bevacizumab products can increase the risk of hemorrhage. Advise patients to immediately contact their healthcare provider for signs and symptoms of serious or unusual bleeding including coughing or spitting blood [see Warnings and Precautions (5.3)].

Arterial and Venous Thromboembolic Events

Bevacizumab products increase the risk of arterial and venous thromboembolic events. Advise patients to immediately contact their healthcare provider for signs and symptoms of arterial or venous thromboembolism [see Warnings and Precautions (5.4, 5.5)].

Hypertension

Bevacizumab products can increase blood pressure. Advise patients that they will undergo routine blood pressure monitoring and to contact their healthcare provider if they experience changes in blood pressure [see Warnings and Precautions (5.6)].

Posterior Reversible Leukoencephalopathy Syndrome

Posterior reversible encephalopathy syndrome (PRES) has been associated with bevacizumab products treatment. Advise patients to immediately contact their healthcare provider for new onset or worsening neurological function [see Warnings and Precautions (5.7)].

Renal Injury and Proteinuria

Bevacizumab products increase the risk of proteinuria and renal injury, including nephrotic syndrome. Advise patients that treatment with ZIRABEV requires regular monitoring of renal function and to contact their healthcare provider for proteinuria or signs and symptoms of nephrotic syndrome [see Warnings and Precautions (5.8)].

Infusion-Related Reactions

Bevacizumab products can cause infusion-related reactions. Advise patients to contact their healthcare provider immediately for signs or symptoms of infusion-related reactions [see Warnings and Precautions (5.9)].

Congestive Heart Failure

Bevacizumab products can increase the risk of developing congestive heart failure. Advise patients to contact their healthcare provider immediately for signs and symptoms of CHF [see Warnings and Precautions (5.12)].

Embryo-Fetal Toxicity

Advise female patients that bevacizumab products may cause fetal harm and to inform their healthcare provider with a known or suspected pregnancy [see Warnings and Precautions (5.10), Use in Specific Populations (8.1)]. Advise females of reproductive potential to use effective contraception during treatment with ZIRABEV and for 6 months after the last dose [see Use in Specific Populations (8.3)].

Ovarian Failure

Bevacizumab products may lead to ovarian failure. Advise patients of potential options for preservation of ova prior to starting treatment [see Warnings and Precautions (5.11)].

Lactation

Advise women not to breastfeed during treatment with ZIRABEV and for 6 months after the last dose [see Use in Specific Populations (8.2)].

This product's labeling may have been updated. For the most recent prescribing information, please visit www.pfizer.com.

For medical information about ZIRABEV, please visit www.pfizermedinfo.com or call 1-800-438-1985.

Manufactured by
Pfizer Inc.
New York, NY 10001
US License No. 2001

Distributed by
Pfizer Labs
Division of Pfizer Inc.
New York, NY 10001

LAB-1185-6.0

PRINCIPAL DISPLAY PANEL - 4 mL Vial Label

NDC 0069-0315-01
Rx only

Zirabev™
(bevacizumab–bvzr)
Injection

100 mg/4 mL
(25 mg/mL)

For Intravenous Infusion
After Dilution
One SINGLE-DOSE VIAL
DISCARD UNUSED PORTION.

PRINCIPAL DISPLAY PANEL - 4 mL Vial Carton

NDC 0069-0315-01

Zirabev™
(bevacizumab–bvzr)
Injection

100 mg/4 mL
(25 mg/mL)

For Intravenous Infusion
After Dilution

One SINGLE-DOSE VIAL

DISCARD UNUSED PORTION.

Rx only

Pfizer Oncology

PRINCIPAL DISPLAY PANEL - 16 mL Vial Label

NDC 0069-0342-01
Rx only

Zirabev™
(bevacizumab–bvzr)
Injection

400 mg/16 mL
(25 mg/mL)

For Intravenous Infusion
After Dilution
One SINGLE-DOSE VIAL
DISCARD UNUSED PORTION.

PRINCIPAL DISPLAY PANEL - 16 mL Vial Carton

NDC 0069-0342-01

Zirabev™
(bevacizumab–bvzr)
Injection

400 mg/16 mL
(25 mg/mL)

For Intravenous Infusion
After Dilution

One SINGLE-DOSE VIAL

DISCARD UNUSED PORTION.

Rx only

Pfizer Oncology